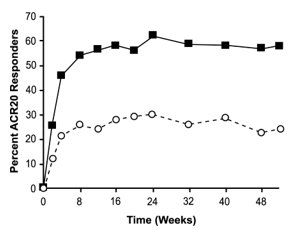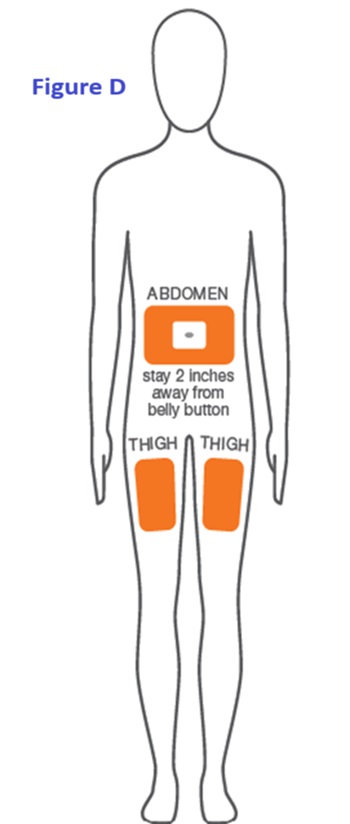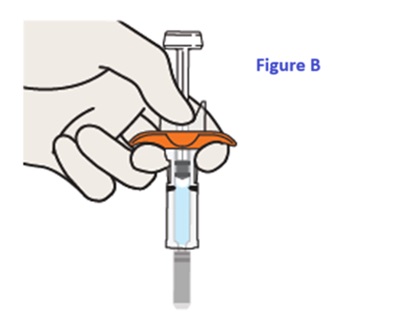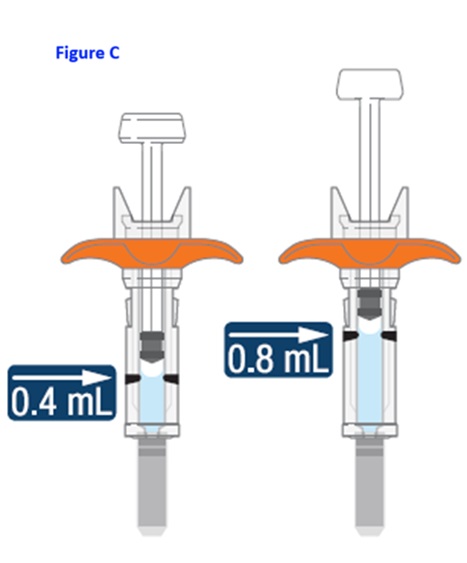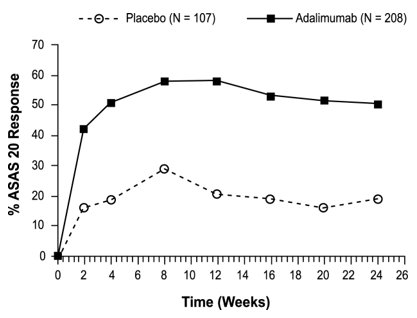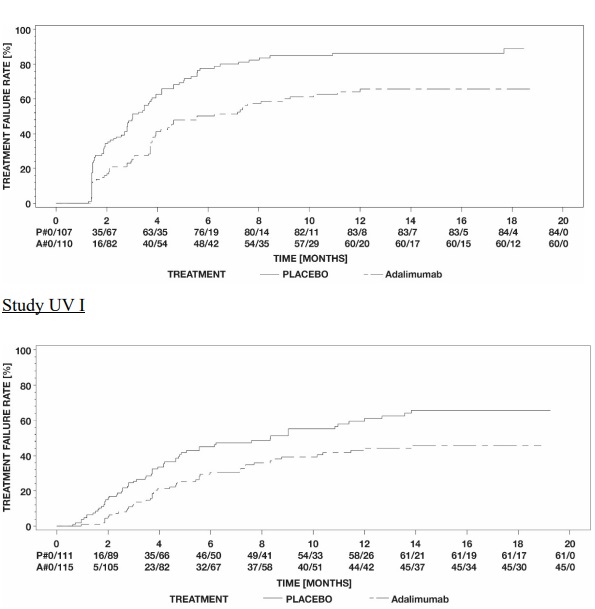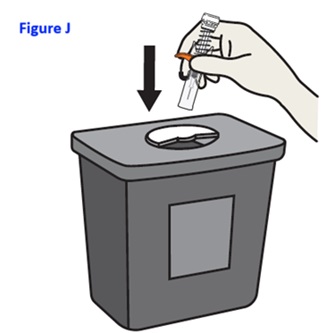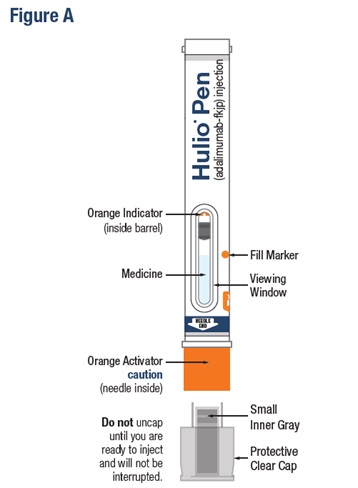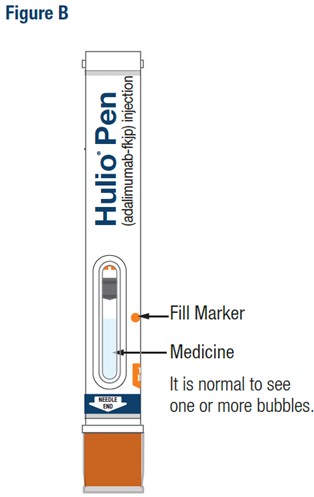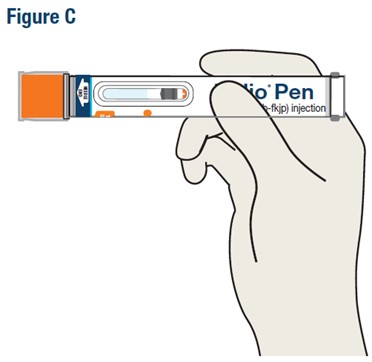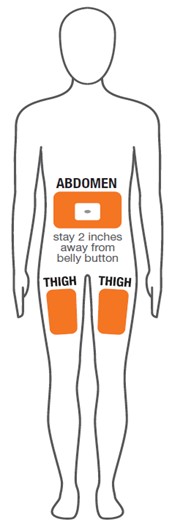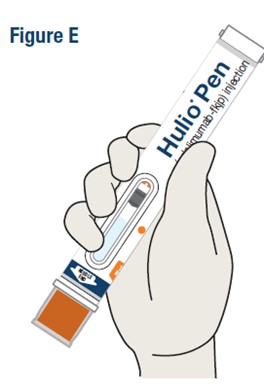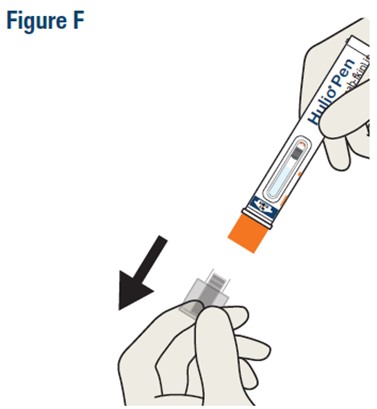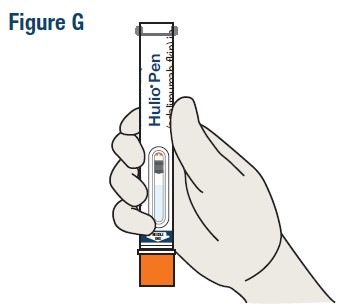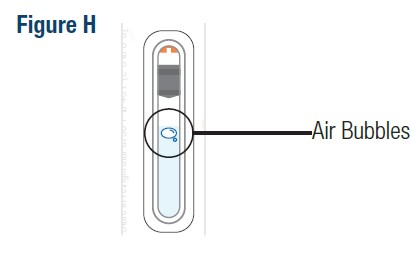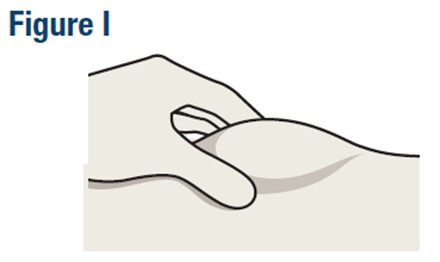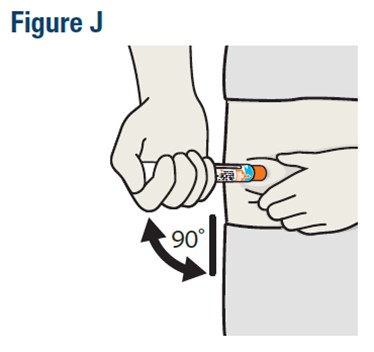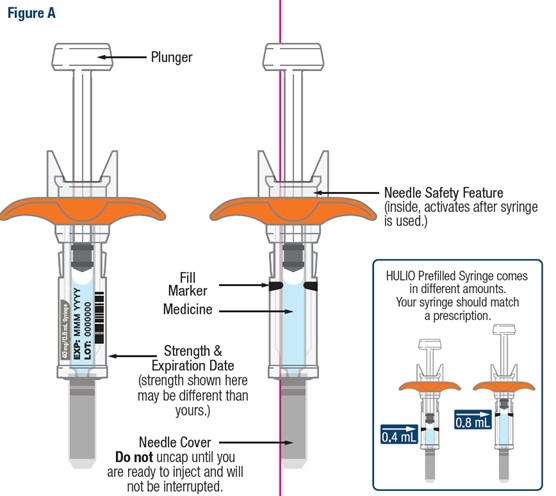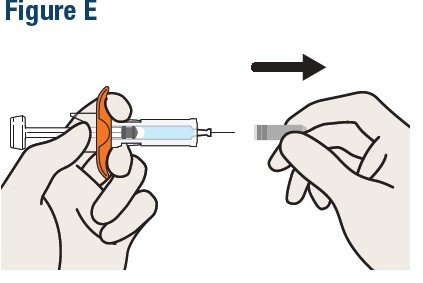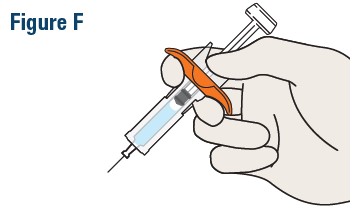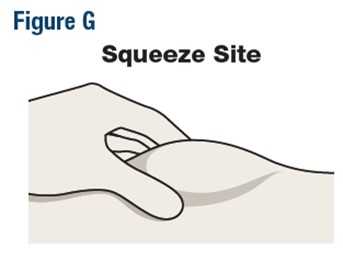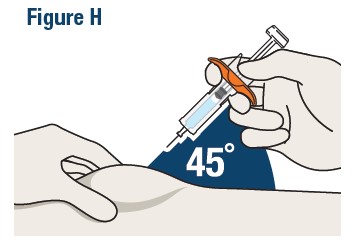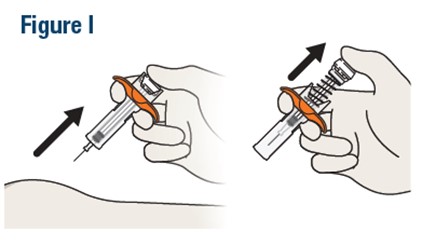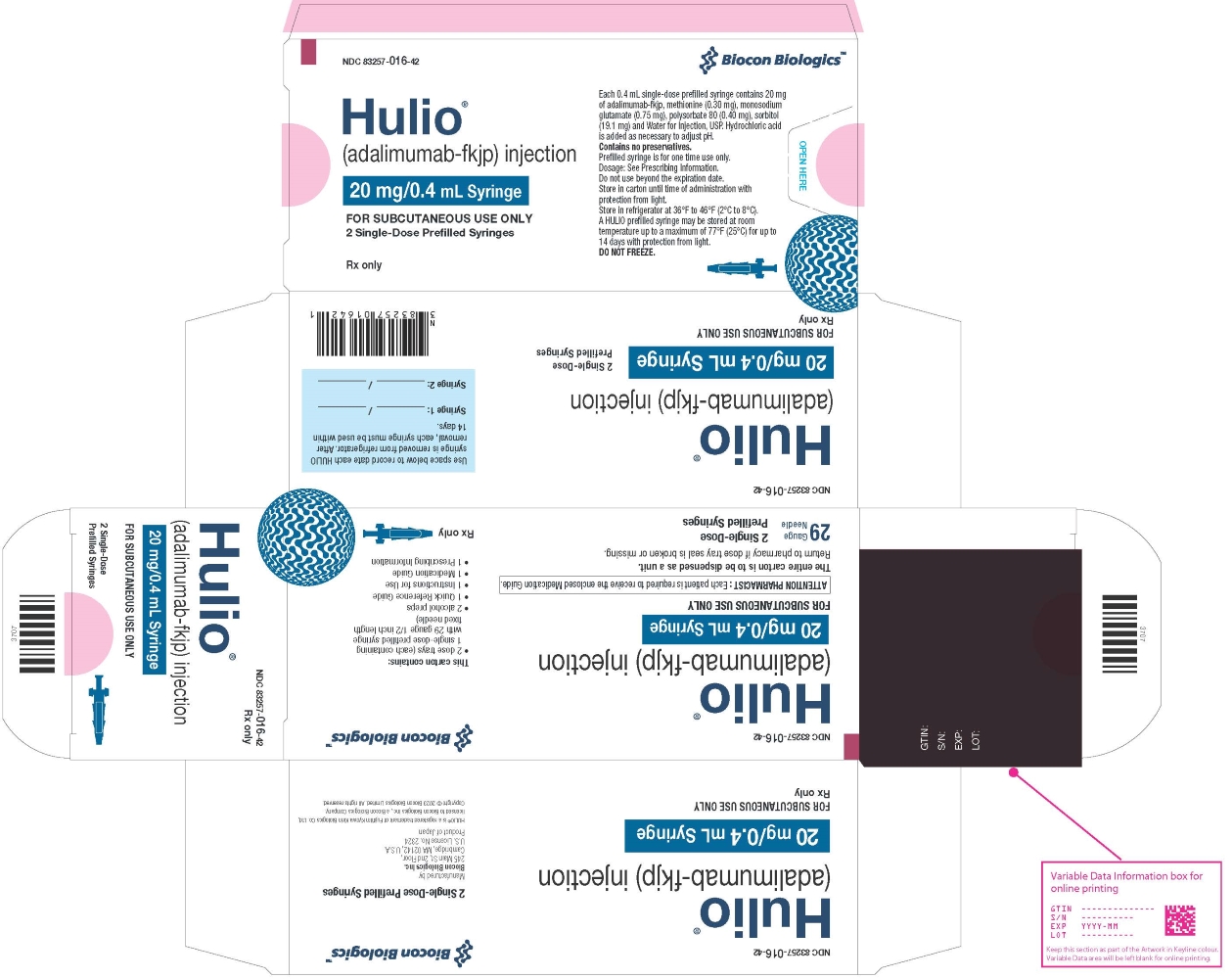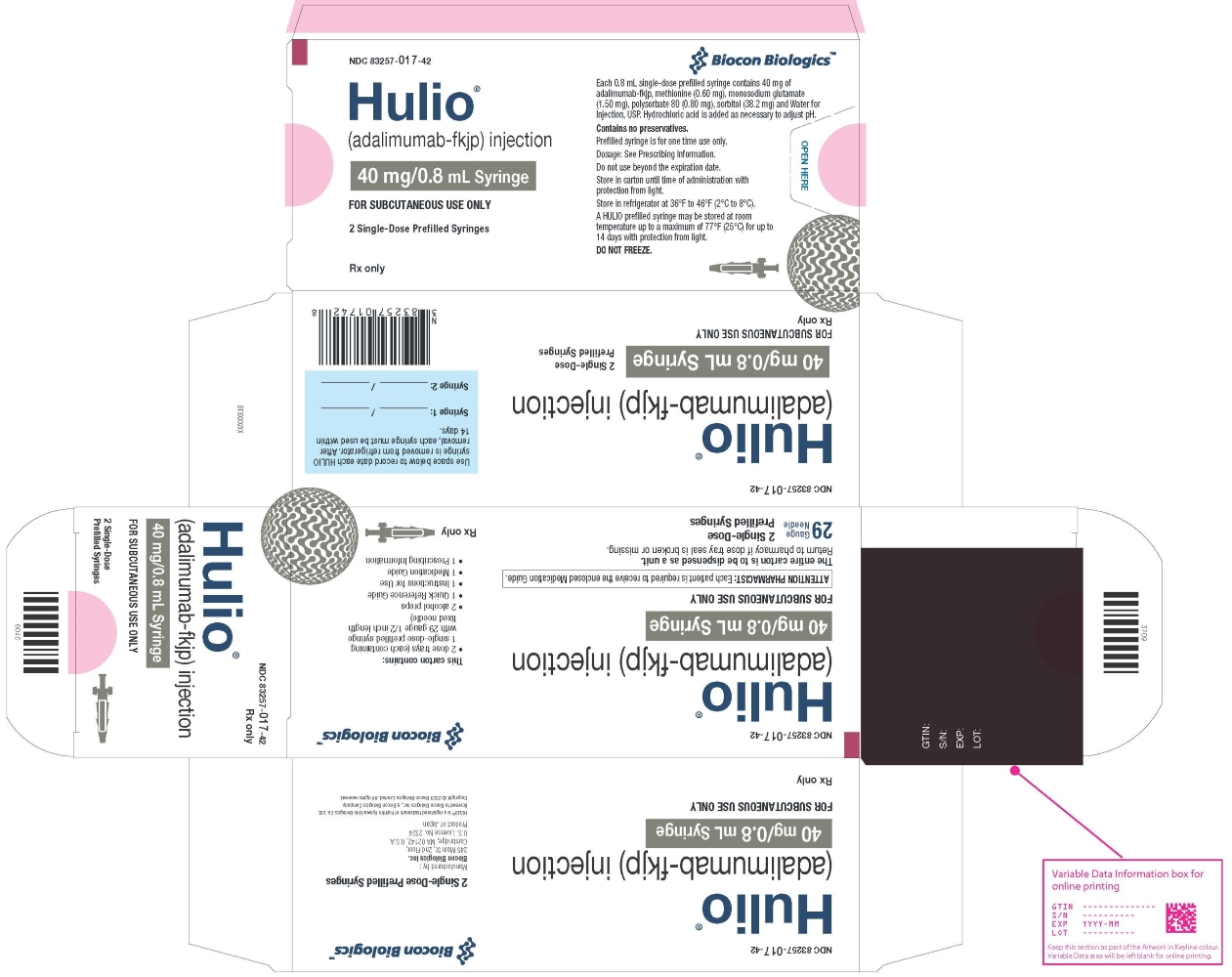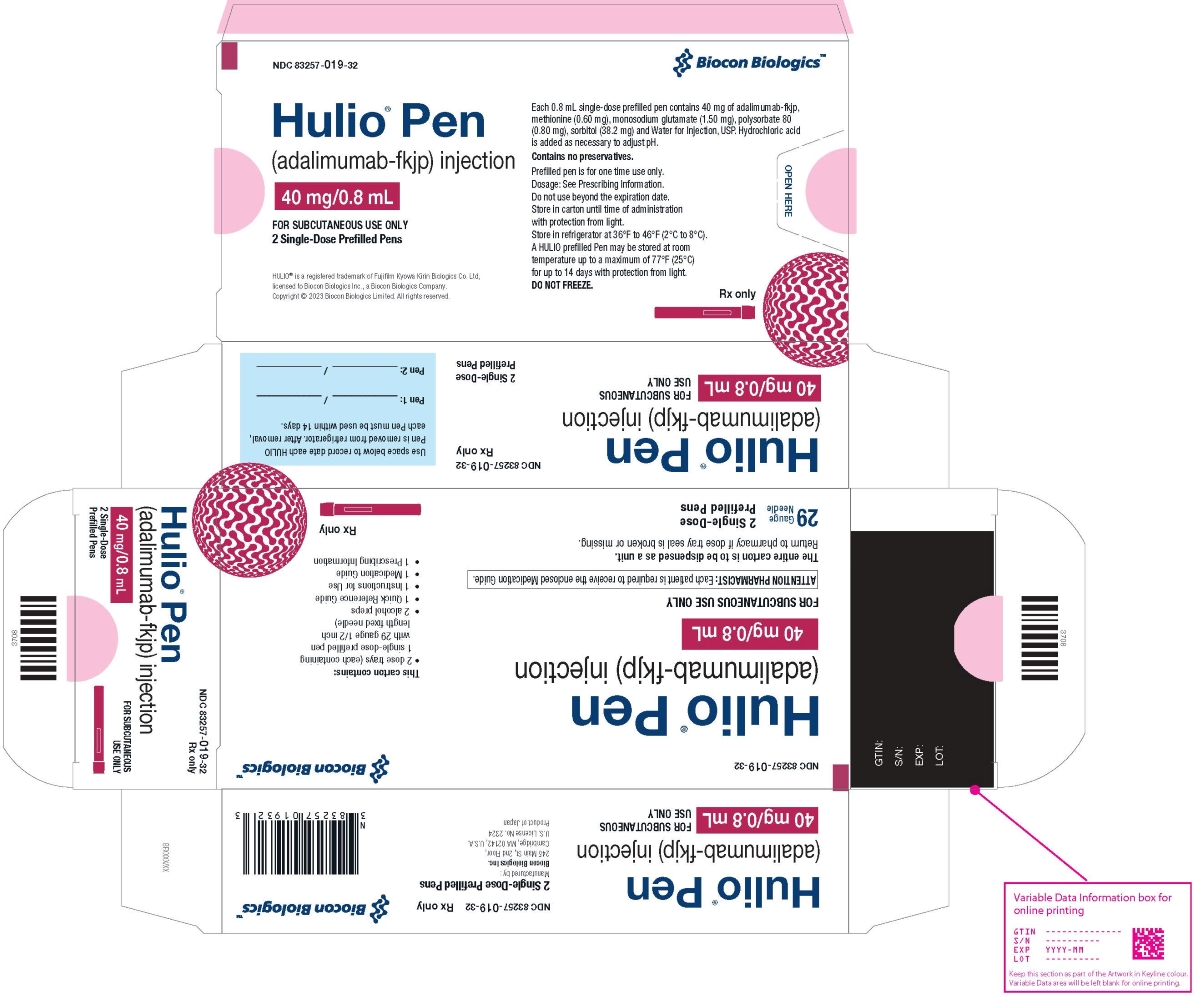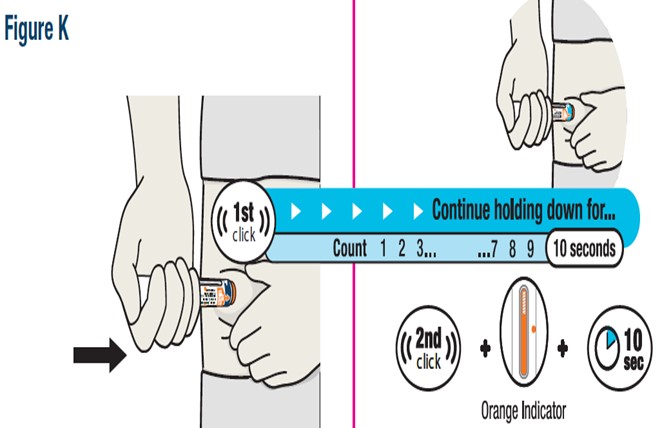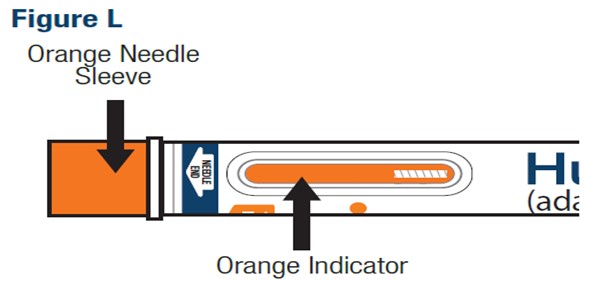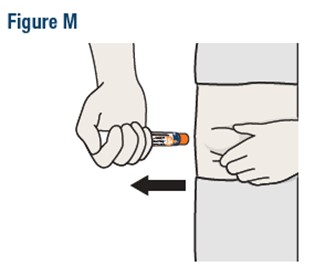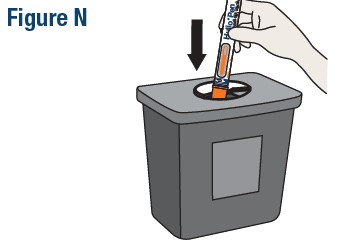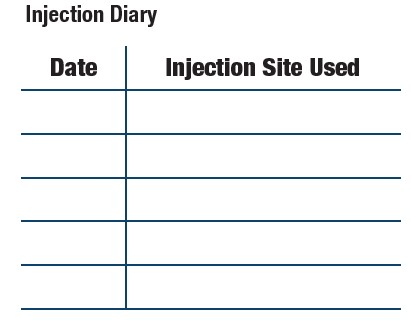 DRUG LABEL: HULIO
NDC: 83257-016 | Form: KIT | Route: SUBCUTANEOUS
Manufacturer: Biocon Biologics Inc
Category: prescription | Type: HUMAN PRESCRIPTION DRUG LABEL
Date: 20250206

ACTIVE INGREDIENTS: ADALIMUMAB 20 mg/0.4 mL; ISOPROPYL ALCOHOL 0.70 mg/1 mL
INACTIVE INGREDIENTS: METHIONINE 0.30 mg/0.4 mL; MONOSODIUM GLUTAMATE 0.75 mg/0.4 mL; POLYSORBATE 80 0.40 mg/0.4 mL; SORBITOL 19.1 mg/0.4 mL; WATER; WATER

HIGHLIGHTS OF PRESCRIBING INFORMATION

These highlights do not include all the information needed to use HULIO safely and effectively. See full prescribing information for HULIO.
HULIO® (adalimumab-fkjp) injection, for subcutaneous use
Initial U.S. Approval: 2020
HULIO® (adalimumab-fkjp) is biosimilar* to HUMIRA (adalimumab)

WARNING: SERIOUS INFECTIONS and MALIGNANCY

See full prescribing information for complete boxed warning.

SERIOUS INFECTIONS (5.1, 6.1):

- Increased risk of serious infections leading to hospitalization or death, including tuberculosis (TB), bacterial sepsis, invasive fungal infections (such as histoplasmosis), and infections due to other opportunistic pathogens.
- Discontinue HULIO if a patient develops a serious infection or sepsis during treatment.
- Perform test for latent TB; if positive, start treatment for TB prior to starting HULIO.
- Monitor all patients for active TB during treatment, even if initial latent TB test is negative.

MALIGNANCY (5.2):

- Lymphoma and other malignancies, some fatal, have been reported in children and adolescent patients treated with TNF blockers including adalimumab products.
- Post-marketing cases of hepatosplenic T-cell lymphoma (HSTCL), a rare type of T-cell lymphoma, have occurred in adolescent and young adults with inflammatory bowel disease treated with TNF blockers including adalimumab products.

1 INDICATIONS AND USAGE

HULIO is a tumor necrosis factor (TNF) blocker indicated for:

- Rheumatoid Arthritis (RA) (1.1): reducing signs and symptoms, inducing major clinical response, inhibiting the progression of structural damage, and improving physical function in adult patients with moderately to severely active RA.
- Juvenile Idiopathic Arthritis (JIA) (1.2): reducing signs and symptoms of moderately to severely active polyarticular JIA in patients 2 years of age and older.
- Psoriatic Arthritis (PsA) (1.3): reducing signs and symptoms, inhibiting the progression of structural damage, and improving physical function in adult patients with active PsA.
- Ankylosing Spondylitis (AS) (1.4): reducing signs and symptoms in adult patients with active AS.
- Crohn’s Disease (CD) (1.5): treatment of moderately to severely active Crohn’s disease in adults and pediatric patients 6 years of age and older.
- Ulcerative Colitis (UC) (1.6): treatment of moderately to severely active ulcerative colitis in adult patients.
- Limitations of Use: Effectiveness has not been established in patients who have lost response to or were intolerant to TNF blockers.
- Plaque Psoriasis (Ps) (1.7): treatment of adult patients with moderate to severe chronic plaque psoriasis who are candidates for systemic therapy or phototherapy, and when other systemic therapies are medically less appropriate.
- Hidradenitis Suppurativa (HS) (1.8): treatment of moderate to severe hidradenitis suppurativa in adult patients.
- Uveitis (UV) (1.9): treatment of non-infectious intermediate, posterior, and panuveitis in adult patients.

2 DOSAGE AND ADMINISTRATION

- Administer by subcutaneous injection (2)

Rheumatoid Arthritis, Psoriatic Arthritis, Ankylosing Spondylitis (2.1):

- Adults: 40 mg every other week.
  - Some patients with RA not receiving methotrexate may benefit from increasing the dosage to 40 mg every week or 80 mg every other week.

Juvenile Idiopathic Arthritis (2.2):

Pediatric Weight; 2 Years of Age and Older | Recommended Dosage
15 kg (33 lbs) to less than 30 kg (66 lbs) | 20 mg every other week
30 kg (66 lbs) and greater | 40 mg every other week

Crohn’s Disease (2.3):

- Adults: 160 mg on Day 1 (given in one day or split over two consecutive days); 80 mg on Day 15; and 40 mg every other week starting on Day 29.
- Pediatric Patients 6 Years of Age and Older:

Pediatric Weight | Recommended Dosage
Pediatric Weight | Days 1 and 15 | Starting on Day 29
17 kg (37 lbs); to less than; 40 kg (88 lbs) | Day 1: 80 mg; Day 15: 40 mg | 20 mg every other week
40 kg (88 lbs); and greater | Day 1: 160 mg (single dose or split over two consecutive days); Day 15: 80 mg | 40 mg every other week

Ulcerative Colitis (2.4):

- Adults: 160 mg on Day 1 (given in one day or split over two consecutive days), 80 mg on Day 15 and 40 mg every other week starting on Day 29. Discontinue in patients without evidence of clinical remission by eight weeks (Day 57).

Plaque Psoriasis or Adult Uveitis (2.5):

- Adults: 80 mg initial dose, followed by 40 mg every other week starting one week after initial dose.

Hidradenitis Suppurativa (2.6):

- Adults:
  - Day 1: 160 mg (given in one day or split over two consecutive days)
  - Day 15: 80 mg
  - Day 29 and subsequent doses: 40 mg every week or 80 mg every other week

3 DOSAGE FORMS AND STRENGTHS

- Injection: 40 mg/0.8 mL in a single-dose prefilled pen (HULIO Pen) (3)
- Injection: 40 mg/0.8 mL in a single-dose prefilled plastic syringe (3)
- Injection: 20 mg/0.4 mL in a single-dose prefilled plastic syringe (3)

4 CONTRAINDICATIONS

None. (4)

5 WARNINGS AND PRECAUTIONS

- Serious infections: Do not start HULIO during an active infection. If an infection develops, monitor carefully, and stop HULIO if infection becomes serious. (5.1)
- Invasive fungal infections: For patients who develop a systemic illness on HULIO, consider empiric antifungal therapy for those who reside or travel to regions where mycoses are endemic. (5.1)
- Malignancies: Incidence of malignancies was greater in adalimumab-treated patients than in controls. (5.2)
- Anaphylaxis or serious hypersensitivity reactions may occur. (5.3)
- Hepatitis B virus reactivation: Monitor HBV carriers during and several months after therapy. If reactivation occurs, stop HULIO and begin antiviral therapy. (5.4)
- Demyelinating disease: Exacerbation or new onset, may occur. (5.5)
- Cytopenias, pancytopenia: Advise patients to seek immediate medical attention if symptoms develop, and consider stopping HULIO. (5.6)
- Heart failure: Worsening or new onset, may occur. (5.8)
- Lupus-like syndrome: Stop HULIO if syndrome develops. (5.9)

6 ADVERSE REACTIONS

Most common adverse reactions (>10%) are: infections (e.g. upper respiratory, sinusitis), injection site reactions, headache and rash. (6.1)

To report SUSPECTED ADVERSE REACTIONS, contact Biocon Biologics at 1-833-986-1468 or FDA at 1-800-FDA-1088 or www.fda.gov/medwatch.

7 DRUG INTERACTIONS

- Abatacept: Increased risk of serious infection. (5.1, 5.11, 7.2)
- Anakinra: Increased risk of serious infection. (5.1, 5.7, 7.2)
- Live vaccines: Avoid use with HULIO. (5.10, 7.3)

*Biosimilar means that the biological product is approved based on data demonstrating that it is highly similar to an FDA-approved biological product, known as a reference product, and that there are no clinically meaningful differences between the biosimilar product and the reference product.

Biosimilarity of HULIO has been demonstrated for the condition(s) of use (e.g. indication(s), dosing regimen(s)), strength(s), dosage form(s), and route(s) of administration described in its Full Prescribing Information.

FULL PRESCRIBING INFORMATION

WARNING: SERIOUS INFECTIONS and MALIGNANCY

SERIOUS INFECTIONS

Patients treated with adalimumab products including HULIO are at increased risk for developing serious infections that may lead to hospitalization or death [see Warnings and Precautions (5.1)]. Most patients who developed these infections were taking concomitant immunosuppressants such as methotrexate or corticosteroids.

Discontinue HULIO if a patient develops a serious infection or sepsis.

Reported infections include:

- Active tuberculosis (TB), including reactivation of latent TB. Patients with TB have frequently presented with disseminated or extrapulmonary disease. Test patients for latent TB before HULIO use and during therapy. Initiate treatment for latent TB prior to HULIO use.
- Invasive fungal infections, including histoplasmosis, coccidioidomycosis, candidiasis, aspergillosis, blastomycosis, and pneumocystosis. Patients with histoplasmosis or other invasive fungal infections may present with disseminated, rather than localized, disease. Antigen and antibody testing for histoplasmosis may be negative in some patients with active infection. Consider empiric anti-fungal therapy in patients at risk for invasive fungal infections who develop severe systemic illness.
- Bacterial, viral and other infections due to opportunistic pathogens, including Legionella and Listeria.

Carefully consider the risks and benefits of treatment with HULIO prior to initiating therapy in patients with chronic or recurrent infection.

Monitor patients closely for the development of signs and symptoms of infection during and after treatment with HULIO, including the possible development of TB in patients who tested negative for latent TB infection prior to initiating therapy [see Warnings and Precautions (5.1) and Adverse Reactions (6.1)].

MALIGNANCY

Lymphoma and other malignancies, some fatal, have been reported in children and adolescent patients treated with TNF blockers including adalimumab products [see Warnings and Precautions (5.2)]. Post-marketing cases of hepatosplenic T-cell lymphoma (HSTCL), a rare type of T-cell lymphoma, have been reported in patients treated with TNF blockers including adalimumab products. These cases have had a very aggressive disease course and have been fatal. The majority of reported TNF blocker cases have occurred in patients with Crohn's disease or ulcerative colitis and the majority were in adolescent and young adult males. Almost all these patients had received treatment with azathioprine or 6-mercaptopurine (6–MP) concomitantly with a TNF blocker at or prior to diagnosis. It is uncertain whether the occurrence of HSTCL is related to use of a TNF blocker or a TNF blocker in combination with these other immunosuppressants [see Warnings and Precautions (5.2)].

1 INDICATIONS AND USAGE

1.1 Rheumatoid Arthritis

HULIO is indicated for reducing signs and symptoms, inducing major clinical response, inhibiting the progression of structural damage, and improving physical function in adult patients with moderately to severely active rheumatoid arthritis. HULIO can be used alone or in combination with methotrexate or other non-biologic disease-modifying anti-rheumatic drugs (DMARDs).

1.2 Juvenile Idiopathic Arthritis

HULIO is indicated for reducing signs and symptoms of moderately to severely active polyarticular juvenile idiopathic arthritis in patients 2 years of age and older. HULIO can be used alone or in combination with methotrexate.

1.3 Psoriatic Arthritis

HULIO is indicated for reducing signs and symptoms, inhibiting the progression of structural damage, and improving physical function in adult patients with active psoriatic arthritis. HULIO can be used alone or in combination with non-biologic DMARDs.

1.4 Ankylosing Spondylitis

HULIO is indicated for reducing signs and symptoms in adult patients with active ankylosing spondylitis.

1.5 Crohn’s Disease

HULIO is indicated for the treatment of moderately to severely active Crohn’s disease in adults and pediatric patients 6 years of age and older.

1.6 Ulcerative Colitis

HULIO is indicated for the treatment of moderately to severely active ulcerative colitis in adult patients.

Limitations of Use

The effectiveness of adalimumab products has not been established in patients who have lost response to or were intolerant to TNF blockers [see Clinical Studies (14.7)].

1.7 Plaque Psoriasis

HULIO is indicated for the treatment of adult patients with moderate to severe chronic plaque psoriasis who are candidates for systemic therapy or phototherapy, and when other systemic therapies are medically less appropriate. HULIO should only be administered to patients who will be closely monitored and have regular follow-up visits with a physician [see Warnings and Precautions (5)].

1.8 Hidradenitis Suppurativa

HULIO is indicated for the treatment of moderate to severe hidradenitis suppurativa in adult patients.

1.9 Uveitis

HULIO is indicated for the treatment of non-infectious intermediate, posterior, and panuveitis in adult patients.

2 DOSAGE AND ADMINISTRATION

2.1 Rheumatoid Arthritis, Psoriatic Arthritis, and Ankylosing Spondylitis

The recommended subcutaneous dosage of HULIO for adult patients with rheumatoid arthritis (RA), psoriatic arthritis (PsA), or ankylosing spondylitis (AS) is 40 mg administered every other week. Methotrexate (MTX), other non-biologic DMARDS, glucocorticoids, nonsteroidal anti-inflammatory drugs (NSAIDs), and/or analgesics may be continued during treatment with HULIO. In the treatment of RA, some patients not taking concomitant MTX may derive additional benefit from increasing the dosage of HULIO to 40 mg every week or 80 mg every other week.

2.2 Juvenile Idiopathic Arthritis

The recommended subcutaneous dosage of HULIO for patients 2 years of age and older with polyarticular juvenile idiopathic arthritis (JIA) is based on weight as shown below. MTX, glucocorticoids, NSAIDs, and/or analgesics may be continued during treatment with HULIO.

Pediatric Weight; (2 Years of Age and older) | Recommended Dosage
15 kg (33 lbs) to less than 30 kg (66 lbs) | 20 mg every other week
30 kg (66 lbs) and greater | 40 mg every other week

There is no dosage form for HULIO that allows weight-based dosing for pediatric patients below 15 kg.

Adalimumab products have not been studied in patients with polyarticular JIA less than 2 years of age or in patients with a weight below 10 kg.

2.3 Crohn’s Disease

Adults

The recommended subcutaneous dosage of HULIO for adult patients with Crohn’s disease (CD) is 160 mg initially on Day 1 (given in one day or split over two consecutive days), followed by 80 mg two weeks later (Day 15). Two weeks later (Day 29) begin a dosage of 40 mg every other week. Aminosalicylates and/or corticosteroids may be continued during treatment with HULIO. Azathioprine, 6-mercaptopurine (6-MP) [see Warnings and Precautions (5.2)] or MTX may be continued during treatment with HULIO if necessary.

Pediatrics

The recommended subcutaneous dosage of HULIO for pediatric patients 6 years of age and older with Crohn’s disease (CD) is based on body weight as shown below:

Pediatric Weight | Recommended Dosage
Pediatric Weight | Days 1 through 15 | Starting on Day 29
17 kg (37 lbs) to; less than 40 kg (88 lbs) | Day 1: 80 mg; Day 15: 40 mg | 20 mg every other week
40 kg (88 lbs) and greater | Day 1: 160 mg (single dose or split; over two consecutive days); Day 15: 80 mg | 40 mg every other week

2.4 Ulcerative Colitis

Adults

The recommended subcutaneous dosage of HULIO for adult patients with ulcerative colitis is 160 mg initially on Day 1 (given in one day or split over two consecutive days), followed by 80 mg two weeks later (Day 15). Two weeks later (Day 29) continue with a dosage of 40 mg every other week.

Discontinue HULIO in adult patients without evidence of clinical remission by eight weeks (Day 57) of therapy. Aminosalicylates and/or corticosteroids may be continued during treatment with HULIO. Azathioprine and 6-mercaptopurine (6-MP) [see Warnings and Precautions (5.2)] may be continued during treatment with HULIO if necessary.

2.5 Plaque Psoriasis or Adult Uveitis

The recommended subcutaneous dosage of HULIO for adult patients with plaque psoriasis (Ps) or Uveitis (UV) is an initial dose of 80 mg, followed by 40 mg given every other week starting one week after the initial dose. The use of adalimumab products in moderate to severe chronic Ps beyond one year has not been evaluated in controlled clinical studies.

2.6 Hidradenitis Suppurativa

Adults

The recommended subcutaneous dosage of HULIO for adult patients with hidradenitis suppurativa (HS) is an initial dose of 160 mg (given in one day or split over two consecutive days), followed by 80 mg two weeks later (Day 15). Begin 40 mg weekly or 80 mg every other week dosing two weeks later (Day 29).

2.7 Monitoring to Assess Safety

Prior to initiating HULIO and periodically during therapy, evaluate patients for active tuberculosis and test for latent infection [see Warnings and Precautions (5.1)].

2.8 General Considerations for Administration

HULIO is intended for use under the guidance and supervision of a physician. A patient may self-inject HULIO or a caregiver may inject HULIO using either the HULIO Pen or prefilled syringe if a physician determines that it is appropriate, and with medical follow-up, as necessary, after proper training in subcutaneous injection technique.

HULIO can be taken out of the refrigerator for 15 to 30 minutes before injecting to allow the liquid to come to room temperature. Do not remove the cap or cover while allowing it to reach room temperature. Carefully inspect the solution in the HULIO Pen or prefilled syringe for particulate matter and discoloration prior to subcutaneous administration. If particulates and discolorations are noted, do not use the product. HULIO does not contain preservatives; therefore, discard unused portions of drug remaining from the syringe.

Instruct patients using the HULIO Pen or prefilled syringe to inject the full amount in the syringe, according to the directions provided in the Instructions for Use [see Instructions for Use].

Injections should occur at separate sites in the thigh or abdomen. Rotate injection sites and do not give injections into areas where the skin is tender, bruised, red or hard.

If a dose is missed, administer the dose as soon as possible. Thereafter, resume dosing at the regular scheduled time.

3 DOSAGE FORMS AND STRENGTHS

HULIO is a clear to slightly opalescent, colorless to pale brownish-yellow solution available as:

- Pen (HULIO Pen)
  Injection: 40 mg/0.8 mL in a single-dose pen.
- Prefilled Syringe
  Injection: 40 mg/0.8 mL in a single-dose prefilled plastic syringe.
  Injection: 20 mg/0.4 mL in a single-dose prefilled plastic syringe.

4 CONTRAINDICATIONS

None.

5 WARNINGS AND PRECAUTIONS

5.1 Serious Infections

Patients treated with adalimumab products including HULIO are at increased risk for developing serious infections involving various organ systems and sites that may lead to hospitalization or death. Opportunistic infections due to bacterial, mycobacterial, invasive fungal, viral, parasitic, or other opportunistic pathogens including aspergillosis, blastomycosis, candidiasis, coccidioidomycosis, histoplasmosis, legionellosis, listeriosis, pneumocystosis and tuberculosis have been reported with TNF blockers. Patients have frequently presented with disseminated rather than localized disease.

The concomitant use of a TNF blocker and abatacept or anakinra was associated with a higher risk of serious infections in patients with rheumatoid arthritis (RA); therefore, the concomitant use of HULIO and these biologic products is not recommended in the treatment of patients with RA [see Warnings and Precautions (5.7, 5.11) and Drug Interactions (7.2)].

Treatment with HULIO should not be initiated in patients with an active infection, including localized infections. Patients 65 years of age and older, patients with co-morbid conditions and/or patients taking concomitant immunosuppressants (such as corticosteroids or methotrexate), may be at greater risk of infection. Consider the risks and benefits of treatment prior to initiating therapy in patients:

- with chronic or recurrent infection;
- who have been exposed to tuberculosis;
- with a history of an opportunistic infection;
- who have resided or traveled in areas of endemic tuberculosis or endemic mycoses, such as histoplasmosis, coccidioidomycosis, or blastomycosis; or
- with underlying conditions that may predispose them to infection.

Tuberculosis

Cases of reactivation of tuberculosis and new onset tuberculosis infections have been reported in patients receiving adalimumab products, including patients who have previously received treatment for latent or active tuberculosis. Reports included cases of pulmonary and extrapulmonary (i.e., disseminated) tuberculosis. Evaluate patients for tuberculosis risk factors and test for latent infection prior to initiating HULIO and periodically during therapy.

Treatment of latent tuberculosis infection prior to therapy with TNF blocking agents has been shown to reduce the risk of tuberculosis reactivation during therapy. Prior to initiating HULIO, assess if treatment for latent tuberculosis is needed; and consider an induration of ≥ 5 mm a positive tuberculin skin test result, even for patients previously vaccinated with Bacille Calmette- Guerin (BCG).

Consider anti-tuberculosis therapy prior to initiation of HULIO in patients with a past history of latent or active tuberculosis in whom an adequate course of treatment cannot be confirmed, and for patients with a negative test for latent tuberculosis but having risk factors for tuberculosis infection. Despite prophylactic treatment for tuberculosis, cases of reactivated tuberculosis have occurred in patients treated with adalimumab products. Consultation with a physician with expertise in the treatment of tuberculosis is recommended to aid in the decision whether initiating anti-tuberculosis therapy is appropriate for an individual patient.

Strongly consider tuberculosis in the differential diagnosis in patients who develop a new infection during HULIO treatment, especially in patients who have previously or recently traveled to countries with a high prevalence of tuberculosis, or who have had close contact with a person with active tuberculosis.

Monitoring

Closely monitor patients for the development of signs and symptoms of infection during and after treatment with HULIO, including the development of tuberculosis in patients who tested negative for latent tuberculosis infection prior to initiating therapy. Tests for latent tuberculosis infection may also be falsely negative while on therapy with HULIO.

Discontinue HULIO if a patient develops a serious infection or sepsis. For a patient who develops a new infection during treatment with HULIO, closely monitor them, perform a prompt and complete diagnostic workup appropriate for an immunocompromised patient, and initiate appropriate antimicrobial therapy.

Invasive Fungal Infections

If patients develop a serious systemic illness and they reside or travel in regions where mycoses are endemic, consider invasive fungal infection in the differential diagnosis. Antigen and antibody testing for histoplasmosis may be negative in some patients with active infection. Consider appropriate empiric antifungal therapy, taking into account both the risk for severe fungal infection and the risks of antifungal therapy, while a diagnostic workup is being performed. To aid in the management of such patients, consider consultation with a physician with expertise in the diagnosis and treatment of invasive fungal infections.

5.2 Malignancies

Consider the risks and benefits of TNF-blocker treatment including HULIO prior to initiating therapy in patients with a known malignancy other than a successfully treated non-melanoma skin cancer (NMSC) or when considering continuing a TNF blocker in patients who develop a malignancy.

Malignancies in Adults

In the controlled portions of clinical trials of some TNF-blockers, including adalimumab products, more cases of malignancies have been observed among TNF-blocker-treated adult patients compared to control-treated adult patients. During the controlled portions of 39 global adalimumab clinical trials in adult patients with rheumatoid arthritis (RA), psoriatic arthritis (PsA), ankylosing spondylitis (AS), Crohn’s disease (CD), ulcerative colitis (UC), plaque psoriasis (Ps), hidradenitis suppurativa (HS), uveitis (UV), malignancies, other than non-melanoma (basal cell and squamous cell) skin cancer, were observed at a rate (95% confidence interval) of 0.7 (0.48, 1.03) per 100 patient-years among 7973 adalimumab-treated patients versus a rate of 0.7 (0.41, 1.17) per 100 patient-years among 4848 control-treated patients (median duration of treatment of 4 months for adalimumab-treated patients and 4 months for control-treated patients). In 52 global controlled and uncontrolled clinical trials of adalimumab in adult patients with RA, PsA, AS, CD, UC, Ps, HS and UV the most frequently observed malignancies, other than lymphoma and NMSC, were breast, colon, prostate, lung, and melanoma. The malignancies in adalimumab-treated patients in the controlled and uncontrolled portions of the studies were similar in type and number to what would be expected in the general U.S. population according to the SEER database (adjusted for age, gender, and race).^1

In controlled trials of other TNF blockers in adult patients at higher risk for malignancies (i.e., patients with COPD with a significant smoking history and cyclophosphamide-treated patients with Wegener’s granulomatosis), a greater portion of malignancies occurred in the TNF blocker group compared to the control group.

Non-Melanoma Skin Cancer

During the controlled portions of 39 global adalimumab clinical trials in adult patients with RA, PsA, AS, CD, UC, Ps, HS and UV, the rate (95% confidence interval) of NMSC was 0.8 (0.52, 1.09) per 100 patient-years among adalimumab-treated patients and 0.2 (0.10, 0.59) per 100 patient-years among control-treated patients. Examine all patients, and in particular patients with a medical history of prior prolonged immunosuppressant therapy or psoriasis patients with a history of PUVA treatment for the presence of NMSC prior to and during treatment with HULIO.

Lymphoma and Leukemia

In the controlled portions of clinical trials of all the TNF-blockers in adults, more cases of lymphoma have been observed among TNF-blocker-treated patients compared to control-treated patients. In the controlled portions of 39 global adalimumab clinical trials in adult patients with RA, PsA, AS, CD, UC, Ps, HS and UV, 2 lymphomas occurred among 7973 adalimumab-treated patients versus 1 among 4848 control-treated patients. In 52 global controlled and uncontrolled clinical trials of adalimumab in adult patients with RA, PsA, AS, CD, UC, Ps, HS and UV with a median duration of approximately 0.7 years, including 24,605 patients and over 40,215 patient-years of adalimumab, the observed rate of lymphomas was approximately 0.11 per 100 patient-years. This is approximately 3-fold higher than expected in the general U.S. population according to the SEER database (adjusted for age, gender, and race).^1 Rates of lymphoma in clinical trials of adalimumab cannot be compared to rates of lymphoma in clinical trials of other TNF blockers and may not predict the rates observed in a broader patient population. Patients with RA and other chronic inflammatory diseases, particularly those with highly active disease and/or chronic exposure to immunosuppressant therapies, may be at a higher risk (up to several fold) than the general population for the development of lymphoma, even in the absence of TNF blockers. Post-marketing cases of acute and chronic leukemia have been reported in association with TNF-blocker use in RA and other indications. Even in the absence of TNF-blocker therapy, patients with RA may be at a higher risk (approximately 2-fold) than the general population for the development of leukemia.

Malignancies in Pediatric Patients and Young Adults

Malignancies, some fatal, have been reported among children, adolescents, and young adults who received treatment with TNF-blockers (initiation of therapy ≤ 18 years of age), of which HULIO is a member. Approximately half the cases were lymphomas, including Hodgkin's and non-Hodgkin's lymphoma. The other cases represented a variety of different malignancies and included rare malignancies usually associated with immunosuppression and malignancies that are not usually observed in children and adolescents. The malignancies occurred after a median of 30 months of therapy (range 1 to 84 months). Most of the patients were receiving concomitant immunosuppressants. These cases were reported post-marketing and are derived from a variety of sources including registries and spontaneous postmarketing reports.

Postmarketing cases of hepatosplenic T-cell lymphoma (HSTCL), a rare type of T-cell lymphoma, have been reported in patients treated with TNF blockers including adalimumab products. These cases have had a very aggressive disease course and have been fatal. The majority of reported TNF blocker cases have occurred in patients with Crohn's disease or ulcerative colitis and the majority were in adolescent and young adult males. Almost all of these patients had received treatment with the immunosuppressants azathioprine or 6-mercaptopurine (6–MP) concomitantly with a TNF blocker at or prior to diagnosis. It is uncertain whether the occurrence of HSTCL is related to use of a TNF blocker or a TNF blocker in combination with these other immunosuppressants. The potential risk with the combination of azathioprine or 6- mercaptopurine and HULIO should be carefully considered.

5.3 Hypersensitivity Reactions

Anaphylaxis and angioneurotic edema have been reported following administration of adalimumab products. If an anaphylactic or other serious allergic reaction occurs, immediately discontinue administration of HULIO and institute appropriate therapy. In clinical trials of adalimumab, hypersensitivity reactions (e.g., rash, anaphylactoid reaction, fixed drug reaction, non-specified drug reaction, urticaria) have been observed.

5.4 Hepatitis B Virus Reactivation

Use of TNF blockers, including HULIO, may increase the risk of reactivation of hepatitis B virus (HBV) in patients who are chronic carriers of this virus. In some instances, HBV reactivation occurring in conjunction with TNF blocker therapy has been fatal. The majority of these reports have occurred in patients concomitantly receiving other medications that suppress the immune system, which may also contribute to HBV reactivation. Evaluate patients at risk for HBV infection for prior evidence of HBV infection before initiating TNF blocker therapy. Exercise caution in prescribing TNF blockers for patients identified as carriers of HBV. Adequate data are not available on the safety or efficacy of treating patients who are carriers of HBV with anti-viral therapy in conjunction with TNF blocker therapy to prevent HBV reactivation. For patients who are carriers of HBV and require treatment with TNF blockers, closely monitor such patients for clinical and laboratory signs of active HBV infection throughout therapy and for several months following termination of therapy. In patients who develop HBV reactivation, stop HULIO and initiate effective anti-viral therapy with appropriate supportive treatment. The safety of resuming TNF blocker therapy after HBV reactivation is controlled is not known. Therefore, exercise caution when considering resumption of HULIO therapy in this situation and monitor patients closely.

5.5 Neurologic Reactions

Use of TNF blocking agents, including adalimumab products, has been associated with rare cases of new onset or exacerbation of clinical symptoms and/or radiographic evidence of central nervous system demyelinating disease, including multiple sclerosis (MS) and optic neuritis, and peripheral demyelinating disease, including Guillain-Barré syndrome. Exercise caution in considering the use of HULIO in patients with preexisting or recent-onset central or peripheral nervous system demyelinating disorders; discontinuation of HULIO should be considered if any of these disorders develop. There is a known association between intermediate uveitis and central demyelinating disorders.

5.6 Hematological Reactions

Rare reports of pancytopenia including aplastic anemia have been reported with TNF blocking agents. Adverse reactions of the hematologic system, including medically significant cytopenia (e.g., thrombocytopenia, leukopenia) have been infrequently reported with adalimumab products. The causal relationship of these reports to adalimumab products remains unclear. Advise all patients to seek immediate medical attention if they develop signs and symptoms suggestive of blood dyscrasias or infection (e.g., persistent fever, bruising, bleeding, pallor) while on HULIO. Consider discontinuation of HULIO therapy in patients with confirmed significant hematologic abnormalities.

5.7 Increased Risk of Infection when Used with Anakinra

Concurrent use of anakinra (an interleukin-1 antagonist) and another TNF-blocker, was associated with a greater proportion of serious infections and neutropenia and no added benefit compared with the TNF-blocker alone in patients with RA. Therefore, the combination of HULIO and anakinra is not recommended [see Drug Interactions (7.2)].

5.8 Heart Failure

Cases of worsening congestive heart failure (CHF) and new onset CHF have been reported with TNF blockers. Cases of worsening CHF have also been observed with adalimumab products. Adalimumab products have not been formally studied in patients with CHF; however, in clinical trials of another TNF blocker, a higher rate of serious CHF-related adverse reactions was observed. Exercise caution when using HULIO in patients who have heart failure and monitor them carefully.

5.9 Autoimmunity

Treatment with adalimumab products may result in the formation of autoantibodies and, rarely, in the development of a lupus-like syndrome. If a patient develops symptoms suggestive of a lupus-like syndrome following treatment with HULIO, discontinue treatment [see Adverse Reactions (6.1)].

5.10 Immunizations

In a placebo-controlled clinical trial of patients with RA, no difference was detected in anti-pneumococcal antibody response between adalimumab and placebo treatment groups when the pneumococcal polysaccharide vaccine and influenza vaccine were administered concurrently with adalimumab. Similar proportions of patients developed protective levels of anti-influenza antibodies between adalimumab and placebo treatment groups; however, titers in aggregate to influenza antigens were moderately lower in patients receiving adalimumab. The clinical significance of this is unknown. Patients on HULIO may receive concurrent vaccinations, except for live vaccines. No data are available on the secondary transmission of infection by live vaccines in patients receiving adalimumab products.

It is recommended that pediatric patients, if possible, be brought up to date with all immunizations in agreement with current immunization guidelines prior to initiating HULIO therapy. Patients on HULIO may receive concurrent vaccinations, except for live vaccines.

The safety of administering live or live-attenuated vaccines in infants exposed to adalimumab products in utero is unknown. Risks and benefits should be considered prior to vaccinating (live or live attenuated) exposed infants [see Use in Specific Populations (8.1, 8.4)].

5.11 Increased Risk of Infection When Used with Abatacept

In controlled trials, the concurrent administration of TNF-blockers and abatacept was associated with a greater proportion of serious infections than the use of a TNF-blocker alone; the combination therapy, compared to the use of a TNF-blocker alone, has not demonstrated improved clinical benefit in the treatment of RA. Therefore, the combination of abatacept with TNF-blockers including HULIO is not recommended [see Drug Interactions (7.2)].

6 ADVERSE REACTIONS

The following clinically significant adverse reactions are described elsewhere in the labeling:

- Serious Infections [see Warnings and Precautions (5.1)]
- Malignancies [see Warnings and Precautions (5.2)]
- Hypersensitivity Reactions [see Warnings and Precautions (5.3)]
- Hepatitis B Virus Reactivation [see Warnings and Precautions (5.4)]
- Neurologic Reactions [see Warnings and Precautions (5.5)]
- Hematological Reactions [see Warnings and Precautions (5.6)]
- Heart Failure [see Warnings and Precautions (5.8)]
- Autoimmunity [see Warnings and Precautions (5.9)]

6.1 Clinical Trials Experience

Because clinical trials are conducted under widely varying conditions, adverse reaction rates observed in the clinical trials of a drug cannot be directly compared to rates in the clinical trials of another drug and may not reflect the rates observed in practice.

The most common adverse reaction with adalimumab was injection site reactions. In placebo-controlled trials, 20% of patients treated with adalimumab developed injection site reactions (erythema and/or itching, hemorrhage, pain or swelling), compared to 14% of patients receiving placebo. Most injection site reactions were described as mild and generally did not necessitate drug discontinuation.

The proportion of patients who discontinued treatment due to adverse reactions during the double-blind, placebo-controlled portion of studies in patients with RA (i.e., Studies RA-I, RA-II, RA-III and RA-IV) was 7% for patients taking adalimumab and 4% for placebo-treated patients. The most common adverse reactions leading to discontinuation of adalimumab in these RA studies were clinical flare reaction (0.7%), rash (0.3%) and pneumonia (0.3%).

Infections

In the controlled portions of the 39 global adalimumab clinical trials in adult patients with RA, PsA, AS, CD, UC, Ps, HS, UV, the rate of serious infections was 4.3 per 100 patient years in 7973 adalimumab treated patients versus a rate of 2.9 per 100 patient years in 4848 control-treated patients. Serious infections observed included pneumonia, septic arthritis, prosthetic and post-surgical infections, erysipelas, cellulitis, diverticulitis, and pyelonephritis [see Warnings and Precautions (5.1)].

Tuberculosis and Opportunistic Infections

In 52 global controlled and uncontrolled clinical trials in RA, PsA, AS, CD, UC, Ps, HS and UV that included 24,605 adalimumab treated patients, the rate of reported active tuberculosis was 0.20 per 100 patient-years and the rate of positive PPD conversion was 0.09 per 100 patient-years. In a subgroup of 10,113 U.S. and Canadian adalimumab treated patients, the rate of reported active TB was 0.05 per 100 patient-years and the rate of positive PPD conversion was 0.07 per 100 patient-years. These trials included reports of miliary, lymphatic, peritoneal, and pulmonary TB. Most of the TB cases occurred within the first eight months after initiation of therapy and may reflect recrudescence of latent disease. In these global clinical trials, cases of serious opportunistic infections have been reported at an overall rate of 0.05 per 100 patient-years. Some cases of serious opportunistic infections and TB have been fatal [see Warnings and Precautions (5.1)].

Autoantibodies

In the rheumatoid arthritis controlled trials, 12% of patients treated with adalimumab and 7% of placebo-treated patients that had negative baseline ANA titers developed positive titers at week 24. Two patients out of 3046 treated with adalimumab developed clinical signs suggestive of new-onset lupus-like syndrome. The patients improved following discontinuation of therapy. No patients developed lupus nephritis or central nervous system symptoms. The impact of long-term treatment with adalimumab products on the development of autoimmune diseases is unknown.

Liver Enzyme Elevations

There have been reports of severe hepatic reactions including acute liver failure in patients receiving TNF-blockers. In controlled Phase 3 trials of adalimumab (40 mg SC every other week) in patients with RA, PsA, and AS with control period duration ranging from 4 to 104 weeks, ALT elevations ≥ 3 x ULN occurred in 3.5% of adalimumab-treated patients and 1.5% of control-treated patients. Since many of these patients in these trials were also taking medications that cause liver enzyme elevations (e.g., NSAIDS, MTX), the relationship between adalimumab and the liver enzyme elevations is not clear. In a controlled Phase 3 trial of adalimumab in patients with polyarticular JIA who were 4 to 17 years, ALT elevations ≥ 3 x ULN occurred in 4.4% of adalimumab-treated patients and 1.5% of control-treated patients (ALT more common than AST); liver enzyme test elevations were more frequent among those treated with the combination of adalimumab and MTX than those treated with adalimumab alone. In general, these elevations did not lead to discontinuation of adalimumab treatment. No ALT elevations ≥ 3 x ULN occurred in the open-label study of adalimumab in patients with polyarticular JIA who were 2 to < 4 years.

In controlled Phase 3 trials of adalimumab (initial doses of 160 mg and 80 mg, or 80 mg and 40 mg on Days 1 and 15, respectively, followed by 40 mg every other week) in adult patients with Crohn’s Disease with a control period duration ranging from 4 to 52 weeks, ALT elevations ≥ 3 x ULN occurred in 0.9% of adalimumab-treated patients and 0.9% of control-treated patients. In the Phase 3 trial of adalimumab in pediatric patients with Crohn’s disease which evaluated efficacy and safety of two body weight based maintenance dose regimens following body weight based induction therapy up to 52 weeks of treatment, ALT elevations ≥ 3 x ULN occurred in 2.6% (5/192) of patients, of whom 4 were receiving concomitant immunosuppressants at baseline; none of these patients discontinued due to abnormalities in ALT tests. In controlled Phase 3 trials of adalimumab (initial doses of 160 mg and 80 mg on Days 1 and 15 respectively, followed by 40 mg every other week) in adult patients with UC with control period duration ranging from 1 to 52 weeks, ALT elevations ≥3 x ULN occurred in 1.5% of adalimumab-treated patients and 1.0% of control-treated patients. In controlled Phase 3 trials of adalimumab (initial dose of 80 mg then 40 mg every other week) in patients with Ps with control period duration ranging from 12 to 24 weeks, ALT elevations ≥ 3 x ULN occurred in 1.8% of adalimumab-treated patients and 1.8% of control-treated patients. In controlled trials of adalimumab (initial doses of 160 mg at Week 0 and 80 mg at Week 2, followed by 40 mg every week starting at Week 4), in subjects with HS with a control period duration ranging from 12 to 16 weeks, ALT elevations ≥ 3 x ULN occurred in 0.3% of adalimumab-treated subjects and 0.6% of control-treated subjects. In controlled trials of adalimumab (initial doses of 80 mg at Week 0 followed by 40 mg every other week starting at Week 1) in adult patients with uveitis with an exposure of 165.4 PYs and 119.8 PYs in adalimumab-treated and control-treated patients, respectively, ALT elevations ≥ 3 x ULN occurred in 2.4% of adalimumab-treated patients and 2.4% of control-treated patients.

Other Adverse Reactions

Rheumatoid Arthritis Clinical Studies

The data described below reflect exposure to adalimumab in 2468 patients, including 2073 exposed for 6 months, 1497 exposed for greater than one year and 1380 in adequate and well-controlled studies (Studies RA-I, RA-II, RA-III, and RA-IV). Adalimumab was studied primarily in placebo- controlled trials and in long-term follow up studies for up to 36 months duration. The population had a mean age of 54 years, 77% were female, 91% were Caucasian and had moderately to severely active rheumatoid arthritis. Most patients received 40 mg adalimumab every other week [see Clinical Studies (14.1)].

Table 1 summarizes reactions reported at a rate of at least 5% in patients treated with adalimumab 40 mg every other week compared to placebo and with an incidence higher than placebo. In Study RA-III, the types and frequencies of adverse reactions in the second year open-label extension were similar to those observed in the one-year double-blind portion.

Table 1. Adverse Reactions Reported by ≥5% of Patients Treated with Adalimumab During Placebo-Controlled Period of Pooled RA Studies (Studies RA-I, RA-II, RA-III, and RA-IV)
 | Adalimumab; 40 mg subcutaneous; Every Other Week | Placebo
 | (N=705) | (N=690)
Adverse Reaction (Preferred Term)
Respiratory
Upper respiratory infection | 17% | 13%
Sinusitis | 11% | 9%
Flu syndrome | 7% | 6%
Gastrointestinal
Nausea | 9% | 8%
Abdominal pain | 7% | 4%
Laboratory Tests [Laboratory test abnormalities were reported as adverse reactions in European trials]
Laboratory test abnormal | 8% | 7%
Hypercholesterolemia | 6% | 4%
Hyperlipidemia | 7% | 5%
Hematuria | 5% | 4%
Alkaline phosphatase increased | 5% | 3%
Other
Headache | 12% | 8%
Rash | 12% | 6%
Accidental injury | 10% | 8%
Injection site reaction [Does not include injection site erythema, itching, hemorrhage, pain or swelling] | 8% | 1%
Back pain | 6% | 4%
Urinary tract infection | 8% | 5%
Hypertension | 5% | 3%

Less Common Adverse Reactions in Rheumatoid Arthritis Clinical Studies

Other infrequent serious adverse reactions that do not appear in the Warnings and Precautions or Adverse Reaction sections that occurred at an incidence of less than 5% in adalimumab-treated patients in RA studies were:

Body As A Whole: Pain in extremity, pelvic pain, surgery, thorax pain

Cardiovascular System: Arrhythmia, atrial fibrillation, chest pain, coronary artery disorder, heart arrest, hypertensive encephalopathy, myocardial infarct, palpitation, pericardial effusion, pericarditis, syncope, tachycardia

Digestive System: Cholecystitis, cholelithiasis, esophagitis, gastroenteritis, gastrointestinal hemorrhage, hepatic necrosis, vomiting

Endocrine System: Parathyroid disorder

Hemic And Lymphatic System: Agranulocytosis, polycythemia

Metabolic And Nutritional Disorders: Dehydration, healing abnormal, ketosis, paraproteinemia, peripheral edema

Musculo-Skeletal System: Arthritis, bone disorder, bone fracture (not spontaneous), bone necrosis, joint disorder, muscle cramps, myasthenia, pyogenic arthritis, synovitis, tendon disorder

Neoplasia: Adenoma

Nervous System: Confusion, paresthesia, subdural hematoma, tremor

Respiratory System: Asthma, bronchospasm, dyspnea, lung function decreased, pleural effusion

Special Senses: Cataract

Thrombosis: Thrombosis leg

Urogenital System: Cystitis, kidney calculus, menstrual disorder

Juvenile Idiopathic Arthritis Clinical Studies

In general, the adverse reactions in the adalimumab-treated patients in the polyarticular juvenile idiopathic arthritis (JIA) trials (Studies JIA-I and JIA-II) [see Clinical Studies (14.2)] were similar in frequency and type to those seen in adult patients [see Warnings and Precautions (5), Adverse Reactions (6)]. Important findings and differences from adults are discussed in the following paragraphs.

In Study JIA-I, adalimumab was studied in 171 patients who were 4 to 17 years of age, with polyarticular JIA. Severe adverse reactions reported in the study included neutropenia, streptococcal pharyngitis, increased aminotransferases, herpes zoster, myositis, metrorrhagia, and appendicitis. Serious infections were observed in 4% of patients within approximately 2 years of initiation of treatment with adalimumab and included cases of herpes simplex, pneumonia, urinary tract infection, pharyngitis, and herpes zoster.

In Study JIA-I, 45% of patients experienced an infection while receiving adalimumab with or without concomitant MTX in the first 16 weeks of treatment. The types of infections reported in adalimumab-treated patients were generally similar to those commonly seen in polyarticular JIA patients who are not treated with TNF blockers. Upon initiation of treatment, the most common adverse reactions occurring in this patient population treated with adalimumab were injection site pain and injection site reaction (19% and 16%, respectively). A less commonly reported adverse event in patients receiving adalimumab was granuloma annulare which did not lead to discontinuation of adalimumab treatment.

In the first 48 weeks of treatment in Study JIA-I, non-serious hypersensitivity reactions were seen in approximately 6% of patients and included primarily localized allergic hypersensitivity reactions and allergic rash.

In Study JIA-I, 10% of patients treated with adalimumab who had negative baseline anti-dsDNA antibodies developed positive titers after 48 weeks of treatment. No patient developed clinical signs of autoimmunity during the clinical trial.

Approximately 15% of patients treated with adalimumab developed mild-to-moderate elevations of creatine phosphokinase (CPK) in Study JIA-I. Elevations exceeding 5 times the upper limit of normal were observed in several patients. CPK concentrations decreased or returned to normal in all patients. Most patients were able to continue adalimumab without interruption.

In Study JIA-II, adalimumab was studied in 32 patients who were 2 to <4 years of age or 4 years of age and older weighing <15 kg with polyarticular JIA. The safety profile for this patient population was similar to the safety profile seen in patients 4 to 17 years of age with polyarticular JIA.

In Study JIA-II, 78% of patients experienced an infection while receiving adalimumab. These included nasopharyngitis, bronchitis, upper respiratory tract infection, otitis media, and were mostly mild to moderate in severity. Serious infections were observed in 9% of patients receiving adalimumab in the study and included dental caries, rotavirus gastroenteritis, and varicella.

In Study JIA-II, non-serious allergic reactions were observed in 6% of patients and included intermittent urticaria and rash, which were all mild in severity.

Psoriatic Arthritis and Ankylosing Spondylitis Clinical Studies

Adalimumab has been studied in 395 patients with psoriatic arthritis (PsA) in two placebo-controlled trials and in an open label study and in 393 patients with ankylosing spondylitis (AS) in two placebo-controlled studies [see Clinical Studies (14.3, 14.4)]. The safety profile for patients with PsA and AS treated with adalimumab 40 mg every other week was similar to the safety profile seen in patients with RA, adalimumab Studies RA-I through IV.

Crohn’s Disease Clinical Studies

Adults

The safety profile of adalimumab in 1478 adult patients with Crohn’s disease from four placebo-controlled and two open-label extension studies [see Clinical Studies (14.5)] was similar to the safety profile seen in patients with RA.

Pediatric Patients 6 Years to 17 Years

The safety profile of adalimumab in 192 pediatric patients from one double-blind study (Study PCD-I) and one open-label extension study [see Clinical Studies (14.6)] was similar to the safety profile seen in adult patients with Crohn’s disease.

During the 4-week open label induction phase of Study PCD-I, the most common adverse reactions occurring in the pediatric population treated with adalimumab were injection site pain and injection site reaction (6% and 5%, respectively).

A total of 67% of children experienced an infection while receiving adalimumab in Study PCD-I. These included upper respiratory tract infection and nasopharyngitis.

A total of 5% of children experienced a serious infection while receiving adalimumab in Study PCD-I. These included viral infection, device related sepsis (catheter), gastroenteritis, H1N1 influenza, and disseminated histoplasmosis.

In Study PCD-I, allergic reactions were observed in 5% of children which were all non-serious and were primarily localized reactions.

Ulcerative Colitis Clinical Studies

Adults: The safety profile of adalimumab in 1010 adult patients with ulcerative colitis (UC) from two placebo-controlled studies and one open-label extension study [see Clinical Studies (14.7)] was similar to the safety profile seen in patients with RA.

Plaque Psoriasis Clinical Studies

Adalimumab has been studied in 1696 subjects with plaque psoriasis (Ps) in placebo-controlled and open-label extension studies [see Clinical Studies (14.9)]. The safety profile for subjects with Ps treated with adalimumab was similar to the safety profile seen in subjects with RA with the following exceptions. In the placebo-controlled portions of the clinical trials in Ps subjects, adalimumab-treated subjects had a higher incidence of arthralgia when compared to controls (3% vs. 1%).

Hidradenitis Suppurativa Clinical Studies

Adalimumab has been studied in 727 subjects with hidradenitis suppurativa (HS) in three placebo-controlled studies and one open-label extension study [see Clinical Studies (14.10)]. The safety profile for subjects with HS treated with adalimumab weekly was consistent with the known safety profile of adalimumab.

Flare of HS, defined as ≥25% increase from baseline in abscesses and inflammatory nodule counts and with a minimum of 2 additional lesions, was documented in 22 (22%) of the 100 subjects who were withdrawn from adalimumab treatment following the primary efficacy timepoint in two studies.

Uveitis Clinical Studies

Adalimumab has been studied in 464 adult patients with uveitis (UV) in placebo-controlled and open-label extension studies [see Clinical Studies (14.11)]. The safety profile for patients with UV treated with adalimumab was similar to the safety profile seen in patients with RA.

6.2 Immunogenicity

The observed incidence of anti-drug antibodies is highly dependent on the sensitivity and specificity of the assay. Differences in assay methods preclude meaningful comparisons of the incidence of anti-drug antibodies in the studies described below with the incidence of anti-drug antibodies in other studies, including those of adalimumab or of other adalimumab products.

There are two assays that have been used to measure anti-adalimumab antibodies. With the ELISA, antibodies to adalimumab could be detected only when serum adalimumab concentrations were < 2 mcg/mL. The ECL assay can detect anti-adalimumab antibody titers independent of adalimumab concentrations in the serum samples. The incidence of anti-adalimumab antibody (AAA) development in patients treated with adalimumab are presented in Table 2.

Table 2: Anti-Adalimumab Antibody Development Determined by ELISA and ECL Assay in Patients Treated with Adalimumab
Indications |  | Study Duration | Anti-Adalimumab Antibody; Incidence by ELISA (n/N) |  | Anti-Adalimumab; Antibody; Incidence by ECL; Assay (n/N)
Indications |  |  | In all patients who received adalimumab | In patients with serum adalimumab concentrations < 2 mcg/mL
Rheumatoid Arthritis [In patients receiving concomitant methotrexate (MTX), the incidence of anti-adalimumab antibody was 1% compared to 12% with adalimumab monotherapy] |  | 6 to 12; months | 5% (58/1062) | NR | NA
Juvenile; Idiopathic; Arthritis; (JIA) | 4 to 17 years of age [In patients receiving concomitant MTX, the incidence of anti-adalimumab antibody was 6% compared to 26% with adalimumab monotherapy] | 48 weeks | 16% (27/171) | NR | NA
Juvenile; Idiopathic; Arthritis; (JIA) | 2 to 4 years of age or ≥ 4 years of age and weighing < 15 kg | 24 weeks | 7% (1/15) [This patient received concomitant MTX] | NR | NA
Psoriatic Arthritis [In patients receiving concomitant MTX, the incidence of antibody development was 7% compared to 1% in RA] |  | 48 weeks [Subjects enrolled after completing 2 previous studies of 24 weeks or 12 weeks of treatments.] | 13% (24/178) | NR | NA
Ankylosing Spondylitis |  | 24 weeks | 9% (16/185) | NR | NA
Adult Crohn’s Disease |  | 56 weeks | 3% (7/269) | 8% (7/86) | NA
Pediatric Crohn’s Disease |  | 52 weeks | 3% (6/182) | 10% (6/58) | NA
Adult Ulcerative Colitis |  | 52 weeks | 5% (19/360) | 21% (19/92) | NA
Plaque Psoriasis [In plaque psoriasis patients who were on adalimumab monotherapy and subsequently withdrawn from the treatment, the rate of antibodies to adalimumab after retreatment was similar to the rate observed prior to withdrawal] |  | Up to 52 weeks [One 12-week Phase 2 study and one 52-week Phase 3 study] | 8% (77/920) | 21% (77/372) | NA
Hidradenitis Suppurativa |  | 36 weeks | 7% (30/461) | 28% (58/207) [Among subjects in the 2 Phase 3 studies who stopped adalimumab treatment for up to 24 weeks and in whom adalimumab serum levels subsequently declined to <2 mcg/mL (approximately 22% of total subjects studied)] | 61% (272/445) [No apparent association between antibody development and safety was observed]
Non-infectious Uveitis |  | 52 weeks | 5% (12/249) | 21% (12/57) | 40% (99/249) [No correlation of antibody development to safety or efficacy outcomes was observed]
n: number of patients with anti-adalimumab antibody; NR: not reported; NA: Not applicable (not performed)

Rheumatoid Arthritis and Psoriatic Arthritis

Patients in Studies RA-I, RA-II, and RA-III were tested at multiple time points for antibodies to adalimumab using the ELISA during the 6- to 12- month period. No apparent correlation of antibody development to adverse reactions was observed. With monotherapy, patients receiving every other week dosing may develop antibodies more frequently than those receiving weekly dosing. In patients receiving the recommended dosage of 40 mg every other week as monotherapy, the ACR 20 response was lower among antibody-positive patients than among antibody-negative patients. The long-term immunogenicity of adalimumab products is unknown.

6.3 Postmarketing Experience

The following adverse reactions have been identified during post-approval use of adalimumab products. Because these reactions are reported voluntarily from a population of uncertain size, it is not always possible to reliably estimate their frequency or establish a causal relationship to adalimumab products exposure.

Gastrointestinal disorders: Diverticulitis, large bowel perforations including perforations associated with diverticulitis and appendiceal perforations associated with appendicitis, pancreatitis

General disorders and administration site conditions: Pyrexia

Hepato-biliary disorders: Liver failure, hepatitis

Immune system disorders: Sarcoidosis

Neoplasms benign, malignant and unspecified (including cysts and polyps): Merkel Cell Carcinoma (neuroendocrine carcinoma of the skin)

Nervous system disorders: Demyelinating disorders (e.g., optic neuritis, Guillain-Barré syndrome), cerebrovascular accident

Respiratory disorders: Interstitial lung disease, including pulmonary fibrosis, pulmonary embolism

Skin reactions: Stevens Johnson Syndrome, cutaneous vasculitis, erythema multiforme, new or worsening psoriasis (all sub-types including pustular and palmoplantar), alopecia, lichenoid skin reaction

Vascular disorders: Systemic vasculitis, deep vein thrombosis

7 DRUG INTERACTIONS

7.1 Methotrexate

Adalimumab has been studied in rheumatoid arthritis (RA) patients taking concomitant methotrexate (MTX). Although MTX reduced the apparent adalimumab clearance, the data do not suggest the need for dose adjustment of either HULIO or MTX [see Clinical Pharmacology (12.3)].

7.2 Biological Products

In clinical studies in patients with RA, an increased risk of serious infections has been observed with the combination of TNF blockers with anakinra or abatacept, with no added benefit; therefore, use of HULIO with abatacept or anakinra is not recommended in patients with RA [see Warnings and Precautions (5.7, 5.11)]. A higher rate of serious infections has also been observed in patients with RA treated with rituximab who received subsequent treatment with a TNF blocker. There is insufficient information regarding the concomitant use of HULIO and other biologic products for the treatment of RA, PsA, AS, CD, UC, Ps, HS and UV. Concomitant administration of HULIO with other biologic DMARDS (e.g., anakinra and abatacept) or other TNF blockers is not recommended based upon the possible increased risk for infections and other potential pharmacological interactions.

7.3 Live Vaccines

Avoid the use of live vaccines with HULIO [see Warnings and Precautions (5.10)].

7.4 Cytochrome P450 Substrates

The formation of CYP450 enzymes may be suppressed by increased concentrations of cytokines (e.g., TNFα, IL-6) during chronic inflammation. It is possible for products that antagonize cytokine activity, such as adalimumab products, to influence the formation of CYP450 enzymes. Upon initiation or discontinuation of HULIO in patients being treated with CYP450 substrates with a narrow therapeutic index, monitoring of the effect (e.g., warfarin) or drug concentration (e.g., cyclosporine or theophylline) is recommended and the individual dose of the drug product may be adjusted as needed.

8 USE IN SPECIFIC POPULATIONS

8.1 Pregnancy

Risk Summary

Available studies with use of adalimumab during pregnancy do not reliably establish an association between adalimumab and major birth defects. Clinical data are available from the Organization of Teratology Information Specialists (OTIS)/MotherToBaby Pregnancy Registry in pregnant women with rheumatoid arthritis (RA) or Crohn’s disease (CD) treated with adalimumab. Registry results showed a rate of 10% for major birth defects with first trimester use of adalimumab in pregnant women with RA or CD and a rate of 7.5% for major birth defects in the disease matched comparison cohort. The lack of pattern of major birth defects is reassuring and differences between exposure groups may have impacted the occurrence of birth defects (see Data).

Adalimumab is actively transferred across the placenta during the third trimester of pregnancy and may affect immune response in the in-utero exposed infant (see Clinical Considerations). In an embryo-fetal perinatal development study conducted in cynomolgus monkeys, no fetal harm or malformations were observed with intravenous administration of adalimumab during organogenesis and later in gestation, at doses that produced exposures up to approximately 373 times the maximum recommended human dose (MRHD) of 40 mg subcutaneous without methotrexate (see Data).

The estimated background risk of major birth defects and miscarriage for the indicated populations is unknown. All pregnancies have a background risk of birth defect, loss, or other adverse outcomes. In the U.S. general population, the estimated background risk of major birth defects and miscarriage in clinically recognized pregnancies is 2-4% and 15-20%, respectively.

Clinical Considerations

Disease-associated maternal and embryo/fetal risk

Published data suggest that the risk of adverse pregnancy outcomes in women with RA or inflammatory bowel disease (IBD) is associated with increased disease activity. Adverse pregnancy outcomes include preterm delivery (before 37 weeks of gestation), low birth weight (less than 2500 g) infants, and small for gestational age at birth.

Fetal/Neonatal Adverse Reactions

Monoclonal antibodies are increasingly transported across the placenta as pregnancy progresses, with the largest amount transferred during the third trimester (see Data). Risks and benefits should be considered prior to administering live or live-attenuated vaccines to infants exposed to adalimumab products in utero [see Use in Specific Populations (8.4)].

Data

Human Data

A prospective cohort pregnancy exposure registry conducted by OTIS/MotherToBaby in the U.S. and Canada between 2004 and 2016 compared the risk of major birth defects in live-born infants of 221 women (69 RA, 152 CD) treated with adalimumab during the first trimester and 106 women (74 RA, 32 CD) not treated with adalimumab.

The proportion of major birth defects among live-born infants in the adalimumab-treated and untreated cohorts was 10% (8.7% RA, 10.5% CD) and 7.5% (6.8% RA, 9.4% CD), respectively. The lack of pattern of major birth defects is reassuring and differences between exposure groups may have impacted the occurrence of birth defects. This study cannot reliably establish whether there is an association between adalimumab and major birth defects because of methodological limitations of the registry, including small sample size, the voluntary nature of the study, and the non-randomized design.

In an independent clinical study conducted in ten pregnant women with IBD treated with adalimumab, adalimumab concentrations were measured in maternal serum as well as in cord blood (n=10) and infant serum (n=8) on the day of birth. The last dose of adalimumab was given between 1 and 56 days prior to delivery. Adalimumab concentrations were 0.16-19.7 mcg/mL in cord blood, 4.28-17.7 mcg/mL in infant serum, and 0-16.1 mcg/mL in maternal serum. In all but one case, the cord blood concentration of adalimumab was higher than the maternal serum concentration, suggesting adalimumab actively crosses the placenta. In addition, one infant had serum concentrations at each of the following: 6 weeks (1.94 mcg/mL), 7 weeks (1.31 mcg/mL), 8 weeks (0.93 mcg/mL), and 11 weeks (0.53 mcg/mL), suggesting adalimumab can be detected in the serum of infants exposed in utero for at least 3 months from birth.

Animal Data

In an embryo-fetal perinatal development study, pregnant cynomolgus monkeys received adalimumab from gestation days 20 to 97 at doses that produced exposures up to 373 times that achieved with the MRHD without methotrexate (on an AUC basis with maternal IV doses up to 100 mg/kg/week). Adalimumab did not elicit harm to the fetuses or malformations.

8.2 Lactation

Risk Summary

Limited data from case reports in the published literature describe the presence of adalimumab in human milk at infant doses of 0.1% to 1% of the maternal serum concentration. Published data suggest that the systemic exposure to a breastfed infant is expected to be low because adalimumab is a large molecule and is degraded in the gastrointestinal tract. However, the effects of local exposure in the gastrointestinal tract are unknown. There are no reports of adverse effects of adalimumab products on the breastfed infant and no effects on milk production. The developmental and health benefits of breastfeeding should be considered along with the mother’s clinical need for HULIO and any potential adverse effects on the breastfed child from HULIO or from the underlying maternal condition.

8.4 Pediatric Use

The safety and effectiveness of HULIO have been established for:

- reducing signs and symptoms of moderately to severely active polyarticular JIA in pediatric patients 2 years of age and older.
- the treatment of moderately to severely active Crohn’s disease in pediatric patients 6 years of age and older.

Pediatric assessments for HULIO demonstrate that HULIO is safe and effective for additional indications in pediatric patients for which Humira (adalimumab) is approved. However, HULIO is not approved for such indications due to marketing exclusivity for Humira (adalimumab).

Due to their inhibition of TNFα, adalimumab products administered during pregnancy could affect immune response in the in utero-exposed newborn and infant. Data from eight infants exposed to adalimumab in utero suggest adalimumab crosses the placenta [see Use in Specific Populations (8.1)]. The clinical significance of elevated adalimumab concentrations in infants is unknown. The safety of administering live or live-attenuated vaccines in exposed infants is unknown. Risks and benefits should be considered prior to vaccinating (live or live-attenuated) exposed infants.

Post-marketing cases of lymphoma, including hepatosplenic T-cell lymphoma and other malignancies, some fatal, have been reported among children, adolescents, and young adults who received treatment with TNF-blockers including adalimumab products [see Warnings and Precautions (5.2)].

Juvenile Idiopathic Arthritis

In Study JIA-I, adalimumab was shown to reduce signs and symptoms of active polyarticular JIA in patients 4 to 17 years of age [see Clinical Studies (14.2)]. In Study JIA-II, the safety profile for patients 2 to <4 years of age was similar to the safety profile for patients 4 to 17 years of age with polyarticular JIA [see Adverse Reactions (6.1)]. Adalimumab products have not been studied in patients with polyarticular JIA less than 2 years of age or in patients with a weight below 10 kg.

The safety of adalimumab in patients in the polyarticular JIA trials was generally similar to that observed in adults with certain exceptions [see Adverse Reactions (6.1)].

The safety and effectiveness of HULIO have not been established in pediatric patients with JIA less than 2 years of age.

Pediatric Crohn’s Disease

The safety and effectiveness of HULIO for the treatment of moderately to severely active Crohn’s disease have been established in pediatric patients 6 years of age and older. Use of HULIO for this indication is supported by evidence from adequate and well-controlled studies in adults with additional data from a randomized, double-blind, 52-week clinical study of two dose concentrations of adalimumab in 192 pediatric patients (6 years to 17 years of age) [see Adverse Reactions (6.1), Clinical Pharmacology (12.2, 12.3), Clinical Studies (14.6)]. The adverse reaction profile in patients 6 years to 17 years of age was similar to adults.

The safety and effectiveness of HULIO have not been established in pediatric patients with Crohn’s disease less than 6 years of age.

8.5 Geriatric Use

A total of 519 RA patients 65 years of age and older, including 107 patients 75 years of age and older, received adalimumab in clinical studies RA-I through IV. No overall difference in effectiveness was observed between these patients and younger patients. The frequency of serious infection and malignancy among adalimumab treated patients 65 years of age and older was higher than for those less than 65 years of age. Consider the benefits and risks of HULIO in patients 65 years of age and older. In patients treated with HULIO, closely monitor for the development of infection or malignancy [see Warnings and Precautions (5.1, 5.2)].

10 OVERDOSAGE

Doses up to 10 mg/kg have been administered to patients in clinical trials without evidence of dose-limiting toxicities. In case of overdosage, it is recommended that the patient be monitored for any signs or symptoms of adverse reactions or effects and appropriate symptomatic treatment instituted immediately.

11 DESCRIPTION

Adalimumab-fkjp is a tumor necrosis factor blocker. Adalimumab-fkjp is a recombinant human IgG1 monoclonal antibody. Adalimumab-fkjp is produced by recombinant DNA technology in a mammalian cell expression system (Chinese Hamster Ovary Cells) and is purified by a process that includes specific viral inactivation and removal steps. It consists of 1330 amino acids and has a molecular weight of approximately 148 kilodaltons.

HULIO (adalimumab-fkjp) injection is supplied as a sterile, preservative-free solution for subcutaneous administration. The drug product is supplied as either a single-dose, prefilled pen (HULIO Pen) or as a single-dose, 1 mL prefilled plastic syringe. Enclosed within the pen is a single- dose, 1 mL prefilled plastic syringe. The solution of HULIO is clear to slightly opalescent, colorless to pale brownish-yellow, with a pH of about 5.2.

Each 40 mg/0.8 mL prefilled syringe or prefilled pen delivers 0.8 mL (40 mg) of drug product. Each 0.8 mL of HULIO contains adalimumab-fkjp (40 mg), methionine (0.60 mg), monosodium glutamate (1.50 mg), polysorbate 80 (0.80 mg), sorbitol (38.2 mg) and Water for Injection, USP. Hydrochloric acid is added as necessary to adjust pH.

Each 20 mg/0.4 mL prefilled syringe delivers 0.4 mL (20 mg) of drug product. Each 0.4 mL of HULIO contains adalimumab-fkjp (20 mg), methionine (0.30 mg), monosodium glutamate (0.75 mg), polysorbate 80 (0.40 mg), sorbitol (19.1 mg) and Water for Injection, USP. Hydrochloric acid is added as necessary to adjust pH.

12 CLINICAL PHARMACOLOGY

12.1 Mechanism of Action

Adalimumab products bind specifically to TNF-alpha and block its interaction with the p55 and p75 cell surface TNF receptors. Adalimumab products also lyse surface TNF expressing cells in vitro in the presence of complement. Adalimumab products do not bind or inactivate lymphotoxin (TNF-beta). TNF is a naturally occurring cytokine that is involved in normal inflammatory and immune responses. Elevated concentrations of TNF are found in the synovial fluid of patients with RA, JIA, PsA, and AS and play an important role in both the pathologic inflammation and the joint destruction that are hallmarks of these diseases. Increased concentrations of TNF are also found in psoriasis plaques. In Ps, treatment with HULIO may reduce the epidermal thickness and infiltration of inflammatory cells. The relationship between these pharmacodynamic activities and the mechanism(s) by which adalimumab products exert their clinical effects is unknown.

Adalimumab products also modulate biological responses that are induced or regulated by TNF, including changes in the concentrations of adhesion molecules responsible for leukocyte migration (ELAM-1, VCAM-1, and ICAM-1 with an IC50 of 1-2 X 10^-10M).

12.2 Pharmacodynamics

After treatment with adalimumab, a decrease in concentrations of acute phase reactants of inflammation (C-reactive protein [CRP] and erythrocyte sedimentation rate [ESR]) and serum cytokines (IL-6) was observed compared to baseline in patients with rheumatoid arthritis. A decrease in CRP concentrations was also observed in patients with Crohn’s disease, ulcerative colitis and hidradenitis suppurativa. Serum concentrations of matrix metalloproteinases (MMP-1 and MMP-3) that produce tissue remodeling responsible for cartilage destruction were also decreased after adalimumab administration.

12.3 Pharmacokinetics

The pharmacokinetics of adalimumab were linear over the dose range of 0.5 to 10 mg/kg following administration of a single intravenous dose (adalimumab products are not approved for intravenous use). Following 20, 40, and 80 mg every other week and every week subcutaneous administration, adalimumab mean serum trough concentrations at steady state increased approximately proportionally with dose in RA patients. The mean terminal half-life was approximately 2 weeks, ranging from 10 to 20 days across studies. Healthy subjects and patients with RA displayed similar adalimumab pharmacokinetics.

Adalimumab exposure in patients treated with 80 mg every other week is estimated to be comparable with that in patients treated with 40 mg every week.

Absorption

The average absolute bioavailability of adalimumab following a single 40 mg subcutaneous dose was 64%. The mean time to reach the maximum concentration was 5.5 days (131 ± 56 hours) and the maximum serum concentration was 4.7 ± 1.6 mcg/mL in healthy subjects following a single 40 mg subcutaneous administration of adalimumab.

Distribution

The distribution volume (Vss) ranged from 4.7 to 6.0 L following intravenous administration of doses ranging from 0.25 to 10 mg/kg in RA patients.

Elimination

The single dose pharmacokinetics of adalimumab in RA patients were determined in several studies with intravenous doses ranging from 0.25 to 10 mg/kg. The systemic clearance of adalimumab is approximately 12 mL/hr. In long-term studies with dosing more than two years, there was no evidence of changes in clearance over time in RA patients.

Patient Population

Rheumatoid Arthritis and Ankylosing Spondylitis

In patients receiving 40 mg adalimumab every other week, adalimumab mean steady-state trough concentrations were approximately 5 mcg/mL and 8 to 9 mcg/mL, without and with MTX concomitant treatment, respectively. Adalimumab concentrations in the synovial fluid from five rheumatoid arthritis patients ranged from 31 to 96% of those in serum. The pharmacokinetics of adalimumab in patients with AS were similar to those in patients with RA.

Psoriatic Arthritis

In patients receiving 40 mg every other week, adalimumab mean steady-state trough concentrations were 6 to 10 mcg/mL and 8.5 to 12 mcg/mL, without and with MTX concomitant treatment, respectively.

Plaque Psoriasis

Adalimumab mean steady-state trough concentration was approximately 5 to 6 mcg/mL during adalimumab 40 mg every other week treatment.

Adult Uveitis

Adalimumab mean steady concentration was approximately 8 to 10 mcg/mL during adalimumab 40 mg every other week treatment

Adult Hidradenitis Suppurativa

Adalimumab trough concentrations were approximately 7 to 8 mcg/mL at Week 2 and Week 4, respectively, after receiving 160 mg on Week 0 followed by 80 mg on Week 2. Mean steady-state trough concentrations at Week 12 through Week 36 were approximately 7 to 11 mcg/mL during adalimumab 40 mg every week treatment.

Adult Crohn’s Disease

Adalimumab mean trough concentrations were approximately 12 mcg/mL at Week 2 and Week 4 after receiving 160 mg on Week 0 followed by 80 mg on Week 2. Mean steady-state trough concentrations were 7 mcg/mL at Week 24 and Week 56 during adalimumab 40 mg every other week treatment.

Adult Ulcerative Colitis

Adalimumab mean trough concentrations were approximately 12 mcg/mL at Week 2 and Week 4 after receiving 160 mg on Week 0 followed by 80 mg on Week 2. Mean steady-state trough concentrations were approximately 8 mcg/mL and 15 mcg/mL at Week 52 after receiving a dose of adalimumab 40 mg every other week and 40 mg every week, respectively.

Anti-Drug Antibody Effects on Pharmacokinetics

Rheumatoid Arthritis

A trend toward higher apparent clearance of adalimumab in the presence of anti-adalimumab antibodies was identified.

Hidradenitis Suppurativa

In subjects with moderate to severe HS, antibodies to adalimumab were associated with reduced serum adalimumab concentrations. In general, the extent of reduction in serum adalimumab concentrations is greater with increasing titers of antibodies to adalimumab.

Specific Populations

Geriatric Patients

A lower clearance with increasing age was observed in patients with RA aged 40 to >75 years.

Pediatric Patients

Juvenile Idiopathic Arthritis:

- 4 years to 17 years of age: The adalimumab mean steady-state trough concentrations were 6.8 mcg/mL and 10.9 mcg/mL in patients weighing <30 kg receiving 20 mg adalimumab subcutaneously every other week as monotherapy or with concomitant MTX, respectively. The adalimumab mean steady-state trough concentrations were 6.6 mcg/mL and 8.1 mcg/mL in patients weighing ≥30 kg receiving 40 mg adalimumab subcutaneously every other week as monotherapy or with MTX concomitant treatment, respectively.
- 2 years to <4 years of age or 4 years of age and older weighing <15 kg: The adalimumab mean steady-state trough adalimumab concentrations were 6.0 mcg/mL and 7.9 mcg/mL in patients receiving adalimumab subcutaneously every other week as monotherapy or with MTX concomitant treatment, respectively.

Pediatric Crohn's Disease:Adalimumab mean ± SD concentrations were 15.7±6.5 mcg/mL at Week 4 following 160 mg at Week 0 and 80 mg at Week 2, and 10.5±6.0 mcg/mL at Week 52 following 40 mg every other week dosing in patients weighing ≥ 40 kg. Adalimumab mean ± SD concentrations were 10.6±6.1 mcg/mL at Week 4 following dosing 80 mg at Week 0 and 40 mg at Week 2, and 6.9±3.6 mcg/mL at Week 52 following 20 mg every other week dosing in patients weighing < 40 kg.

Male and Female Patients

No gender-related pharmacokinetic differences were observed after correction for a patient’s body weight. Healthy subjects and patients with rheumatoid arthritis displayed similar adalimumab pharmacokinetics.

Patients with Renal or Hepatic Impairment

No pharmacokinetic data are available in patients with hepatic or renal impairment.

Rheumatoid factor or CRP concentrations

Minor increases in apparent clearance were predicted in RA patients receiving doses lower than the recommended dose and in RA patients with high rheumatoid factor or CRP concentrations. These increases are not likely to be clinically important.

Drug Interaction Studies

Methotrexate: MTX reduced adalimumab apparent clearance after single and multiple dosing by 29% and 44% respectively, in patients with RA [see Drug Interactions (7.1)].

13 NONCLINICAL TOXICOLOGY

13.1 Carcinogenesis, Mutagenesis, Impairment of Fertility

Long-term animal studies of adalimumab products have not been conducted to evaluate the carcinogenic potential or its effect on fertility.

14 CLINICAL STUDIES

14.1 Rheumatoid Arthritis

The efficacy and safety of adalimumab were assessed in five randomized, double-blind studies in patients ≥18 years of age with active rheumatoid arthritis (RA) diagnosed according to American College of Rheumatology (ACR) criteria. Patients had at least 6 swollen and 9 tender joints. Adalimumab was administered subcutaneously in combination with methotrexate (MTX) (12.5 to 25 mg, Studies RA-I, RA-III and RA-V) or as monotherapy (Studies RA-II and RA-V) or with other disease-modifying anti-rheumatic drugs (DMARDs) (Study RA-IV).

Study RA-I evaluated 271 patients who had failed therapy with at least one but no more than four DMARDs and had inadequate response to MTX. Doses of 20, 40 or 80 mg of adalimumab or placebo were given every other week for 24 weeks.

Study RA-II evaluated 544 patients who had failed therapy with at least one DMARD. Doses of placebo, 20 or 40 mg of adalimumab were given as monotherapy every other week or weekly for 26 weeks.

Study RA-III evaluated 619 patients who had an inadequate response to MTX. Patients received placebo, 40 mg of adalimumab every other week with placebo injections on alternate weeks, or 20 mg of adalimumab weekly for up to 52 weeks. Study RA-III had an additional primary endpoint at 52 weeks of inhibition of disease progression (as detected by X-ray results). Upon completion of the first 52 weeks, 457 patients enrolled in an open-label extension phase in which 40 mg of adalimumab was administered every other week for up to 5 years.

Study RA-IV assessed safety in 636 patients who were either DMARD-naive or were permitted to remain on their pre-existing rheumatologic therapy provided that therapy was stable for a minimum of 28 days. Patients were randomized to 40 mg of adalimumab or placebo every other week for 24 weeks.

Study RA-V evaluated 799 patients with moderately to severely active RA of less than 3 years duration who were ≥18 years old and MTX naïve. Patients were randomized to receive either MTX (optimized to 20 mg/week by week 8), adalimumab 40 mg every other week or adalimumab/MTX combination therapy for 104 weeks. Patients were evaluated for signs and symptoms, and for radiographic progression of joint damage. The median disease duration among patients enrolled in the study was 5 months. The median MTX dose achieved was 20 mg.

Clinical Response

The percent of adalimumab treated patients achieving ACR 20, 50 and 70 responses in Studies RA-II and III are shown in Table 3.

Table 3. ACR Responses in Studies RA-II and RA-III (Percent of Patients)
 | Study RA-II; Monotherapy; (26 weeks) |  |  | Study RA-III; Methotrexate Combination; (24 and 52 weeks)
Response | Placebo | Adalimumab | Adalimumab | Placebo/MTX | Adalimumab/MTX
 |  | 40 mg every | 40 mg weekly |  | 40 mg every
 |  | other week |  |  | other week
 | N=110 | N=113 | N=103 | N=200 | N=207
ACR20
Month 6 | 19% | 46% [p<0.01, adalimumab vs. placebo] | 53% | 30% | 63%
Month 12 | NA | NA | NA | 24% | 59%
ACR50
Month 6 | 8% | 22% | 35% | 10% | 39%
Month 12 | NA | NA | NA | 10% | 42%
ACR70
Month 6 | 2% | 12% | 18% | 3% | 21%
Month 12 | NA | NA | NA | 5% | 23%

The results of Study RA-I were similar to Study RA-III; patients receiving adalimumab 40 mg every other week in Study RA-I also achieved ACR 20, 50 and 70 response rates of 65%, 52% and 24%, respectively, compared to placebo responses of 13%, 7% and 3% respectively, at 6 months (p<0.01).

The results of the components of the ACR response criteria for Studies RA-II and RA-III are shown in Table 4. ACR response rates and improvement in all components of ACR response were maintained to week 104. Over the 2 years in Study RA-III, 20% of adalimumab patients receiving 40 mg every other week achieved a major clinical response, defined as maintenance of an ACR 70 response over a 6-month period. ACR responses were maintained in similar proportions of patients for up to 5 years with continuous adalimumab treatment in the open-label portion of Study RA-III.

Table 4. Components of ACR Response in Studies RA-II and RA-III
 | Study RA-II |  |  |  | Study RA-III
Parameter (median) | Placebo; N=110 |  | Adalimumab [40 mg adalimumab administered every other week]; N=113 |  | Placebo/MTX; N=200 |  | Adalimumab/MTX; N=207
 | Baseline | Wk; 26 | Baseline | Wk; 26 | Baseline | Wk; 24 | Baseline | Wk; 24
Number of tender; joints (0-68) | 35 | 26 | 31 | 16 [p<0.001, adalimumab vs. placebo, based on mean change from baseline] | 26 | 15 | 24 | 8
Number of swollen; joints (0-66) | 19 | 16 | 18 | 10 | 17 | 11 | 18 | 5
Physician global; assessment [Visual analogue scale; 0 = best, 10 = worst] | 7.0 | 6.1 | 6.6 | 3.7 | 6.3 | 3.5 | 6.5 | 2.0
Patient global; assessment | 7.5 | 6.3 | 7.5 | 4.5 | 5.4 | 3.9 | 5.2 | 2.0
Pain | 7.3 | 6.1 | 7.3 | 4.1 | 6.0 | 3.8 | 5.8 | 2.1
Disability index; (HAQ) [Disability Index of the Health Assessment Questionnaire; 0 = best, 3 = worst, measures the patient’s ability to perform the following: dress/groom, arise, eat, walk, reach, grip, maintain hygiene, and maintain daily activity] | 2.0 | 1.9 | 1.9 | 1.5 | 1.5 | 1.3 | 1.5 | 0.8
CRP (mg/dL) | 3.9 | 4.3 | 4.6 | 1.8 | 1.0 | 0.9 | 1.0 | 0.4

The time course of ACR 20 response for Study RA-III is shown in Figure 1.

In Study RA-III, 85% of patients with ACR 20 responses at week 24 maintained the response at 52 weeks. The time course of ACR 20 response for Study RA-I and Study RA-II were similar.

Figure 1. Study RA-III ACR 20 Responses over 52 Weeks

In Study RA-IV, 53% of patients treated with adalimumab 40 mg every other week plus standard of care had an ACR 20 response at week 24 compared to 35% on placebo plus standard of care (p<0.001). No unique adverse reactions related to the combination of adalimumab and other DMARDs were observed.

In Study RA-V with MTX naïve patients with recent onset RA, the combination treatment with adalimumab plus MTX led to greater percentages of patients achieving ACR responses than either MTX monotherapy or adalimumab monotherapy at Week 52 and responses were sustained at Week 104 (see Table 5).

Table 5. ACR Response in Study RA-V (Percent of Patients)
Response | MTX [p<0.05, adalimumab/MTX vs. MTX for ACR 20 p<0.001, adalimumab/MTX vs. MTX for ACR 50 and 70, and Major Clinical Response]; N=257 | Adalimumab [p<0.001, adalimumab/MTX vs. adalimumab]; N=274 | Adalimumab/MTX; N=268
ACR20; Week 52; Week 104 | 63%; 56% | 54%; 49% | 73%; 69%
ACR50; Week 52; Week 104 | 46%; 43% | 41%; 37% | 62%; 59%
ACR70; Week 52; Week 104 | 27%; 28% | 26%; 28% | 46%; 47%
Major Clinical Response [Major clinical response is defined as achieving an ACR70 response for a continuous six month period] | 28% | 25% | 49%

At Week 52, all individual components of the ACR response criteria for Study RA-V improved in the adalimumab/MTX group and improvements were maintained to Week 104.

Radiographic Response

In Study RA-III, structural joint damage was assessed radiographically and expressed as change in Total Sharp Score (TSS) and its components, the erosion score and Joint Space Narrowing (JSN) score, at month 12 compared to baseline. At baseline, the median TSS was approximately 55 in the placebo and 40 mg every other week groups. The results are shown in Table 6. Adalimumab/MTX treated patients demonstrated less radiographic progression than patients receiving MTX alone at 52 weeks.

Table 6. Radiographic Mean Changes Over 12 Months in Study RA-III
 | Placebo/MTX | Adalimumab/MTX; 40 mg every; other week | Placebo/MTX-Adalimumab/; MTX (95% Confidence; Interval [95% confidence intervals for the differences in change scores between MTX and adalimumab.]) | P-value [Based on rank analysis]
Total Sharp score | 2.7 | 0.1 | 2.6 (1.4, 3.8) | <0.001
Erosion score | 1.6 | 0.0 | 1.6 (0.9, 2.2) | <0.001
JSN score | 1.0 | 0.1 | 0.9 (0.3, 1.4) | 0.002

In the open-label extension of Study RA-III, 77% of the original patients treated with any dose of adalimumab were evaluated radiographically at 2 years. Patients maintained inhibition of structural damage, as measured by the TSS. Fifty-four percent had no progression of structural damage as defined by a change in the TSS of zero or less. Fifty-five percent (55%) of patients originally treated with 40 mg adalimumab every other week have been evaluated radiographically at 5 years. Patients had continued inhibition of structural damage with 50% showing no progression of structural damage defined by a change in the TSS of zero or less.

In Study RA-V, structural joint damage was assessed as in Study RA-III. Greater inhibition of radiographic progression, as assessed by changes in TSS, erosion score and JSN was observed in the adalimumab/MTX combination group as compared to either the MTX or adalimumab monotherapy group at Week 52 as well as at Week 104 (see Table 7).

Table 7. Radiographic Mean Change [mean (95% confidence interval)] in Study RA-V
 |  | MTX [p<0.001, adalimumab/MTX vs. MTX at 52 and 104 weeks and for adalimumab/MTX vs. adalimumab at 104 weeks]; N=257 | Adalimumab [p<0.01, for adalimumab/MTX vs. adalimumab at 52 weeks]; N=274 | Adalimumab/MTX; N=268
52 Weeks | Total Sharp score | 5.7 (4.2, 7.3) | 3.0 (1.7, 4.3) | 1.3 (0.5, 2.1)
 | Erosion score | 3.7 (2.7, 4.8) | 1.7 (1.0, 2.4) | 0.8 (0.4, 1.2)
 | JSN score | 2.0 (1.2, 2.8) | 1.3 (0.5, 2.1) | 0.5 (0.0, 1.0)
104 Weeks | Total Sharp score | 10.4 (7.7, 13.2) | 5.5 (3.6, 7.4) | 1.9 (0.9, 2.9)
 | Erosion score | 6.4 (4.6, 8.2) | 3.0 (2.0, 4.0) | 1.0 (0.4, 1.6)
 | JSN score | 4.1 (2.7, 5.4) | 2.6 (1.5, 3.7) | 0.9 (0.3, 1.5)

Physical Function Response

In studies RA-I through IV, adalimumab showed significantly greater improvement than placebo in the disability index of Health Assessment Questionnaire (HAQ-DI) from baseline to the end of study, and significantly greater improvement than placebo in the health-outcomes as assessed by The Short Form Health Survey (SF 36). Improvement was seen in both the Physical Component Summary (PCS) and the Mental Component Summary (MCS).

In Study RA-III, the mean (95% CI) improvement in HAQ-DI from baseline at week 52 was 0.60 (0.55, 0.65) for the adalimumab patients and 0.25 (0.17, 0.33) for placebo/MTX (p<0.001) patients. Sixty-three percent of adalimumab-treated patients achieved a 0.5 or greater improvement in HAQ-DI at week 52 in the double-blind portion of the study. Eighty-two percent of these patients maintained that improvement through week 104 and a similar proportion of patients maintained this response through week 260 (5 years) of open-label treatment. Mean improvement in the SF-36 was maintained through the end of measurement at week 156 (3 years).

In Study RA-V, the HAQ-DI and the physical component of the SF-36 showed greater improvement (p<0.001) for the adalimumab/MTX combination therapy group versus either the MTX monotherapy or the adalimumab monotherapy group at Week 52, which was maintained through Week 104.

14.2 Juvenile Idiopathic Arthritis

The safety and efficacy of adalimumab was assessed in two studies (JIA-I and JIA-II) in patients with active polyarticular juvenile idiopathic arthritis (JIA).

Study JIA-I

The safety and efficacy of adalimumab were assessed in a multicenter, randomized, withdrawal, double-blind, parallel-group study in 171 patients who were 4 to 17 years of age with polyarticular JIA. In the study, the patients were stratified into two groups: MTX-treated or non- MTX-treated. All patients had to show signs of active moderate or severe disease despite previous treatment with NSAIDs, analgesics, corticosteroids, or DMARDS. Patients who received prior treatment with any biologic DMARDS were excluded from the study.

The study included four phases: an open-label lead in phase (OL-LI; 16 weeks), a double-blind randomized withdrawal phase (DB; 32 weeks), an open-label extension phase (OLE-BSA; up to 136 weeks), and an open-label fixed dose phase (OLE-FD; 16 weeks). In the first three phases of the study, adalimumab was administered based on body surface area at a dose of 24 mg/m^2 up to a maximum total body dose of 40 mg subcutaneously (SC) every other week. In the OLE-FD phase, the patients were treated with 20 mg of adalimumab SC every other week if their weight was less than 30 kg and with 40 mg of adalimumab SC every other week if their weight was 30 kg or greater. Patients remained on stable doses of NSAIDs and or prednisone (≤0.2 mg/kg/day or 10 mg/day maximum).

Patients demonstrating a Pediatric ACR 30 response at the end of OL-LI phase were randomized into the double blind (DB) phase of the study and received either adalimumab or placebo every other week for 32 weeks or until disease flare. Disease flare was defined as a worsening of ≥30% from baseline in ≥3 of 6 Pediatric ACR core criteria, ≥2 active joints, and improvement of >30% in no more than 1 of the 6 criteria. After 32 weeks or at the time of disease flare during the DB phase, patients were treated in the open-label extension phase based on the BSA regimen (OLE-BSA), before converting to a fixed dose regimen based on body weight (OLE-FD phase).

Study JIA-I Clinical Response

At the end of the 16-week OL-LI phase, 94% of the patients in the MTX stratum and 74% of the patients in the non-MTX stratum were Pediatric ACR 30 responders. In the DB phase significantly fewer patients who received adalimumab experienced disease flare compared to placebo, both without MTX (43% vs. 71%) and with MTX (37% vs. 65%). More patients treated with adalimumab continued to show pediatric ACR 30/50/70 responses at Week 48 compared to patients treated with placebo. Pediatric ACR responses were maintained for up to two years in the OLE phase in patients who received adalimumab throughout the study.

Study JIA-II

Adalimumab was assessed in an open-label, multicenter study in 32 patients who were 2 to <4 years of age or 4 years of age and older weighing <15 kg with moderately to severely active polyarticular JIA. Most patients (97%) received at least 24 weeks of adalimumab treatment dosed 24 mg/m^2 up to a maximum of 20 mg every other week as a single SC injection up to a maximum of 120 weeks duration. During the study, most patients used concomitant MTX, with fewer reporting use of corticosteroids or NSAIDs. The primary objective of the study was evaluation of safety [see Adverse Reactions (6.1)].

14.3 Psoriatic Arthritis

The safety and efficacy of adalimumab was assessed in two randomized, double-blind, placebo controlled studies in 413 patients with psoriatic arthritis (PsA). Upon completion of both studies, 383 patients enrolled in an open-label extension study, in which 40 mg adalimumab was administered every other week.

Study PsA-I enrolled 313 adult patients with moderately to severely active PsA (>3 swollen and >3 tender joints) who had an inadequate response to NSAID therapy in one of the following forms: (1) distal interphalangeal (DIP) involvement (N=23); (2) polyarticular arthritis (absence of rheumatoid nodules and presence of plaque psoriasis) (N=210); (3) arthritis mutilans (N=1); (4) asymmetric PsA (N=77); or (5) AS-like (N=2). Patients on MTX therapy (158 of 313 patients) at enrollment (stable dose of ≤30 mg/week for >1 month) could continue MTX at the same dose. Doses of adalimumab 40 mg or placebo every other week were administered during the 24-week double-blind period of the study.

Compared to placebo, treatment with adalimumab resulted in improvements in the measures of disease activity (see Tables 8 and 9). Among patients with PsA who received adalimumab, the clinical responses were apparent in some patients at the time of the first visit (two weeks) and were maintained up to 88 weeks in the ongoing open-label study. Similar responses were seen in patients with each of the subtypes of psoriatic arthritis, although few patients were enrolled with the arthritis mutilans and ankylosing spondylitis-like subtypes. Responses were similar in patients who were or were not receiving concomitant MTX therapy at baseline.

Patients with psoriatic involvement of at least three percent body surface area (BSA) were evaluated for Psoriatic Area and Severity Index (PASI) responses. At 24 weeks, the proportions of patients achieving a 75% or 90% improvement in the PASI were 59% and 42% respectively, in the adalimumab group (N=69), compared to 1% and 0% respectively, in the placebo group (N=69) (p<0.001). PASI responses were apparent in some patients at the time of the first visit (two weeks). Responses were similar in patients who were or were not receiving concomitant MTX therapy at baseline.

Table 8. ACR Response in Study PsA-I (Percent of Patients)
 | Placebo; N=162 | Adalimumab [p<0.001 for all comparisons between adalimumab and placebo]; N=151
ACR20; Week 12; Week 24 | 14%; 15% | 58%; 57%
ACR50; Week 12; Week 24 | 4%; 6% | 36%; 39%
ACR70; Week 12; Week 24 | 1%; 1% | 20%; 23%

Table 9. Components of Disease Activity in Study PsA-I
 | Placebo; N=162 |  | Adalimumab [p<0.001 for adalimumab vs. placebo comparisons based on median changes]; N=151
Parameter: median | Baseline | 24 weeks | Baseline | 24 weeks
Number of tender joints [Scale 0-78] | 23.0 | 17.0 | 20.0 | 5.0
Number of swollen joints [Scale 0-76] | 11.0 | 9.0 | 11.0 | 3.0
Physician global assessment [Visual analog scale; 0=best, 100=worst] | 53.0 | 49.0 | 55.0 | 16.0
Patient global assessment | 49.5 | 49.0 | 48.0 | 20.0
Pain | 49.0 | 49.0 | 54.0 | 20.0
Disability index (HAQ) [Disability Index of the Health Assessment Questionnaire; 0=best, 3=worst; measures the patient’s ability to perform the following: dress/groom, arise, eat, walk, reach, grip, maintain hygiene, and maintain daily activity.] | 1.0 | 0.9 | 1.0 | 0.4
CRP (mg/dL) [Normal range: 0-0.287 mg/dL] | 0.8 | 0.7 | 0.8 | 0.2

Similar results were seen in an additional, 12-week study in 100 patients with moderate to severe psoriatic arthritis who had suboptimal response to DMARD therapy as manifested by ≥3 tender joints and ≥3 swollen joints at enrollment.

Radiographic Response

Radiographic changes were assessed in the PsA studies. Radiographs of hands, wrists, and feet were obtained at baseline and Week 24 during the double-blind period when patients were on adalimumab or placebo and at Week 48 when all patients were on open-label adalimumab. A modified Total Sharp Score (mTSS), which included distal interphalangeal joints (i.e., not identical to the TSS used for rheumatoid arthritis), was used by readers blinded to treatment group to assess the radiographs.

Adalimumab-treated patients demonstrated greater inhibition of radiographic progression compared to placebo-treated patients and this effect was maintained at 48 weeks (see Table 10).

Table 10. Change in Modified Total Sharp Score in Psoriatic Arthritis
 | Placebo; N=141 | Adalimumab; N=133
 | Week 24 | Week 24 | Week 48
Baseline mean | 22.1 | 23.4 | 23.4
Mean Change ± SD | 0.9 ± 3.1 | -0.1 ± 1.7 | -0.2 ± 4.9 [<0.001 for the difference between adalimumab, Week 48 and Placebo, Week 24 (primary analysis)]

Physical Function Response

In Study PsA-I, physical function and disability were assessed using the HAQ Disability Index (HAQ-DI) and the SF-36 Health Survey. Patients treated with 40 mg of adalimumab every other week showed greater improvement from baseline in the HAQ-DI score (mean decreases of 47% and 49% at Weeks 12 and 24 respectively) in comparison to placebo (mean decreases of 1% and 3% at Weeks 12 and 24 respectively). At Weeks 12 and 24, patients treated with adalimumab showed greater improvement from baseline in the SF-36 Physical Component Summary score compared to patients treated with placebo, and no worsening in the SF-36 Mental Component Summary score. Improvement in physical function based on the HAQ-DI was maintained for up to 84 weeks through the open-label portion of the study.

14.4 Ankylosing Spondylitis

The safety and efficacy of adalimumab 40 mg every other week was assessed in 315 adult patients in a randomized, 24 week double-blind, placebo-controlled study in patients with active ankylosing spondylitis (AS) who had an inadequate response to glucocorticoids, NSAIDs, analgesics, methotrexate or sulfasalazine. Active AS was defined as patients who fulfilled at least two of the following three criteria: (1) a Bath AS disease activity index (BASDAI) score ≥4 cm, (2) a visual analog score (VAS) for total back pain ≥ 40 mm, and (3) morning stiffness ≥ 1 hour. The blinded period was followed by an open-label period during which patients received adalimumab 40 mg every other week subcutaneously for up to an additional 28 weeks.

Improvement in measures of disease activity was first observed at Week 2 and maintained through 24 weeks as shown in Figure 2 and Table 11.

Responses of patients with total spinal ankylosis (n=11) were similar to those without total ankylosis.

Figure 2. ASAS 20 Response By Visit, Study AS-I

At 12 weeks, the ASAS 20/50/70 responses were achieved by 58%, 38%, and 23%, respectively, of patients receiving adalimumab, compared to 21%, 10%, and 5% respectively, of patients receiving placebo (p <0.001). Similar responses were seen at Week 24 and were sustained in patients receiving open-label adalimumab for up to 52 weeks.

A greater proportion of patients treated with adalimumab (22%) achieved a low level of disease activity at 24 weeks (defined as a value <20 [on a scale of 0 to 100 mm] in each of the four ASAS response parameters) compared to patients treated with placebo (6%).

Table 11. Components of Ankylosing Spondylitis Disease Activity
 | Placebo; N=107 |  | Adalimumab; N=208
 | Baseline; mean | Week 24; mean | Baseline; mean | Week 24; mean
ASAS 20 Response Criteria [statistically significant for comparisons between adalimumab and placebo at Week 24]
Patient’s Global Assessment of Disease Activity [Percent of subjects with at least a 20% and 10-unit improvement measured on a Visual Analog Scale (VAS) with 0 = “none” and 100 = “severe”] | 65 | 60 | 63 | 38
Total back pain | 67 | 58 | 65 | 37
Inflammation [mean of questions 5 and 6 of BASDAI (defined in ‘d’)] | 6.7 | 5.6 | 6.7 | 3.6
BASFI [Bath Ankylosing Spondylitis Functional Index] | 56 | 51 | 52 | 34
BASDAI [Bath Ankylosing Spondylitis Disease Activity Index] score | 6.3 | 5.5 | 6.3 | 3.7
BASMI [Bath Ankylosing Spondylitis Metrology Index] score | 4.2 | 4.1 | 3.8 | 3.3
Tragus to wall (cm) | 15.9 | 15.8 | 15.8 | 15.4
Lumbar flexion (cm) | 4.1 | 4.0 | 4.2 | 4.4
Cervical rotation (degrees) | 42.2 | 42.1 | 48.4 | 51.6
Lumbar side flexion (cm) | 8.9 | 9.0 | 9.7 | 11.7
Intermalleolar distance (cm) | 92.9 | 94.0 | 93.5 | 100.8
CRP [C-Reactive Protein (mg/dL)] | 2.2 | 2.0 | 1.8 | 0.6

A second randomized, multicenter, double-blind, placebo-controlled study of 82 patients with ankylosing spondylitis showed similar results.

Patients treated with adalimumab achieved improvement from baseline in the Ankylosing Spondylitis Quality of Life Questionnaire (ASQoL) score (-3.6 vs. -1.1) and in the Short Form Health Survey (SF-36) Physical Component Summary (PCS) score (7.4 vs. 1.9) compared to placebo-treated patients at Week 24.

14.5 Adult Crohn’s Disease

The safety and efficacy of multiple doses of adalimumab were assessed in adult patients with moderately to severely active Crohn’s disease, CD, (Crohn’s Disease Activity Index (CDAI) ≥ 220 and ≤ 450) in randomized, double-blind, placebo-controlled studies. Concomitant stable doses of aminosalicylates, corticosteroids, and/or immunomodulatory agents were permitted, and 79% of patients continued to receive at least one of these medications.

Induction of clinical remission (defined as CDAI < 150) was evaluated in two studies. In Study CD-I, 299 TNF-blocker naïve patients were randomized to one of four treatment groups: the placebo group received placebo at Weeks 0 and 2, the 160/80 group received 160 mg adalimumab at Week 0 and 80 mg at Week 2, the 80/40 group received 80 mg at Week 0 and 40 mg at Week 2, and the 40/20 group received 40 mg at Week 0 and 20 mg at Week 2. Clinical results were assessed at Week 4.

In the second induction study, Study CD-II, 325 patients who had lost response to, or were intolerant to, previous infliximab therapy were randomized to receive either 160 mg adalimumab at Week 0 and 80 mg at Week 2, or placebo at Weeks 0 and 2. Clinical results were assessed at Week 4.

Maintenance of clinical remission was evaluated in Study CD-III. In this study, 854 patients with active disease received open-label adalimumab, 80 mg at week 0 and 40 mg at Week 2. Patients were then randomized at Week 4 to 40 mg adalimumab every other week, 40 mg adalimumab every week, or placebo. The total study duration was 56 weeks. Patients in clinical response (decrease in CDAI ≥70) at Week 4 were stratified and analyzed separately from those not in clinical response at Week 4.

Induction of Clinical Remission

A greater percentage of the patients treated with 160/80 mg adalimumab achieved induction of clinical remission versus placebo at Week 4 regardless of whether the patients were TNF blocker naïve (CD-I), or had lost response to or were intolerant to infliximab (CD-II) (see Table 12).

Table 12. Induction of Clinical Remission in Studies CD-I and CD-II (Percent of Patients)
 | CD-I |  | CD-II
 | Placebo; N=74 | Adalimumab 160/80 mg; N=76 | Placebo; N=166 | Adalimumab 160/80 mg; N=159
Week 4
Clinical remission | 12% | 36% [p<0.001 for adalimumab vs. placebo pairwise comparison of proportions] | 7% | 21%
Clinical response | 34% | 58% [p<0.01 for adalimumab vs. placebo pairwise comparison of proportions] | 34% | 52%
Clinical remission is CDAI score < 150; clinical response is decrease in CDAI of at least 70 points.

Maintenance of Clinical Remission

In Study CD-III at Week 4, 58% (499/854) of patients were in clinical response and were assessed in the primary analysis. At Weeks 26 and 56, greater proportions of patients who were in clinical response at Week 4 achieved clinical remission in the adalimumab 40 mg every other week maintenance group compared to patients in the placebo maintenance group (see Table 13). The group that received adalimumab therapy every week did not demonstrate significantly higher remission rates compared to the group that received adalimumab every other week.

Table 13. Maintenance of Clinical Remission in CD-III (Percent of Patients)
 | Placebo | 40 mg Adalimumab; every other week
 | N=170 | N=172
Week 26
Clinical remission | 17% | 40% [p<0.001 for adalimumab vs. placebo pairwise comparisons of proportions]
Clinical response | 28% | 54%
Week 56
Clinical remission | 12% | 36%
Clinical response | 18% | 43%
Clinical remission is CDAI score < 150; clinical response is decrease in CDAI of at least 70 points.

Of those in response at Week 4 who attained remission during the study, patients in the adalimumab every other week group maintained remission for a longer time than patients in the placebo maintenance group. Among patients who were not in response by Week 12, therapy continued beyond 12 weeks did not result in significantly more responses.

14.6 Pediatric Crohn’s Disease

A randomized, double-blind, 52-week clinical study of 2 dose concentrations of adalimumab (Study PCD-I) was conducted in 192 pediatric patients (6 to 17 years of age) with moderately to severely active Crohn’s disease (defined as Pediatric Crohn’s Disease Activity Index (PCDAI) score > 30). Enrolled patients had over the previous two year period an inadequate response to corticosteroids or an immunomodulator (i.e., azathioprine, 6-mercaptopurine, or methotrexate). Patients who had previously received a TNF blocker were allowed to enroll if they had previously had loss of response or intolerance to that TNF blocker.

Patients received open-label induction therapy at a dose based on their body weight (≥40 kg and <40 kg). Patients weighing ≥40 kg received 160 mg (at Week 0) and 80 mg (at Week 2). Patients weighing <40 kg received 80 mg (at Week 0) and 40 mg (at Week 2). At Week 4, patients within each body weight category (≥40 kg and <40 kg) were randomized 1:1 to one of two maintenance dose regimens (high dose and low dose). The high dose was 40 mg every other week for patients weighing ≥40 kg and 20 mg every other week for patients weighing <40 kg. The low dose was 20 mg every other week for patients weighing ≥40 kg and 10 mg every other week for patients weighing <40 kg.

Concomitant stable dosages of corticosteroids (prednisone dosage ≤40 mg/day or equivalent) and immunomodulators (azathioprine, 6-mercaptopurine, or methotrexate) were permitted throughout the study.

At Week 12, patients who experienced a disease flare (increase in PCDAI of ≥ 15 from Week 4 and absolute PCDAI > 30) or who were non-responders (did not achieve a decrease in the PCDAI of ≥ 15 from baseline for 2 consecutive visits at least 2 weeks apart) were allowed to dose-escalate (i.e., switch from blinded every other week dosing to blinded every week dosing); patients who dose-escalated were considered treatment failures.

At baseline, 38% of patients were receiving corticosteroids, and 62% of patients were receiving an immunomodulator. Forty-four percent (44%) of patients had previously lost response or were intolerant to a TNF blocker. The median baseline PCDAI score was 40.

Of the 192 patients total, 188 patients completed the 4 week induction period, 152 patients completed 26 weeks of treatment, and 124 patients completed 52 weeks of treatment. Fifty-one percent (51%) (48/95) of patients in the low maintenance dose group dose-escalated, and 38% (35/93) of patients in the high maintenance dose group dose-escalated.

At Week 4, 28% (52/188) of patients were in clinical remission (defined as PCDAI ≤ 10).

The proportions of patients in clinical remission (defined as PCDAI ≤ 10) and clinical response (defined as reduction in PCDAI of at least 15 points from baseline) were assessed at Weeks 26 and 52.

At both Weeks 26 and 52, the proportion of patients in clinical remission and clinical response was numerically higher in the high dose group compared to the low dose group (Table 14). The recommended maintenance regimen is 20 mg every other week for patients weighing < 40 kg and 40 mg every other week for patients weighing ≥ 40 kg. Every week dosing is not the recommended maintenance dosing regimen [see Dosage and Administration (2.3)].

Table 14. Clinical Remission and Clinical Response in Study PCD-I
 | Low Maintenance Dose [The low maintenance dose was 20 mg every other week for patients weighing ≥ 40 kg and 10 mg every other week for patients weighing < 40 kg.]; (20 or 10 mg every other week); N = 95 | High Maintenance Dose [The high maintenance dose was 40 mg every other week for patients weighing ≥ 40 kg and 20 mg every other week for patients weighing < 40 kg.]; (40 or 20 mg every other week); N = 93
Week 26
Clinical Remission [Clinical remission defined as PCDAI ≤ 10.] | 28% | 39%
Clinical Response [Clinical response defined as reduction in PCDAI of at least 15 points from baseline.] | 48% | 59%
Week 52
Clinical Remission | 23% | 33%
Clinical Response | 28% | 42%

14.7 Adult Ulcerative Colitis

The safety and efficacy of adalimumab were assessed in adult patients with moderately to severely active ulcerative colitis (Mayo score 6 to 12 on a 12 point scale, with an endoscopy subscore of 2 to 3 on a scale of 0 to 3) despite concurrent or prior treatment with immunosuppressants such as corticosteroids, azathioprine, or 6-MP in two randomized, double-blind, placebo-controlled clinical studies (Studies UC-I and UC-II). Both studies enrolled TNF-blocker naïve patients, but Study UC-II also allowed entry of patients who lost response to or were intolerant to TNF-blockers. Forty percent (40%) of patients enrolled in Study UC-II had previously used another TNF-blocker.

Concomitant stable doses of aminosalicylates and immunosuppressants were permitted. In Studies UC-I and II, patients were receiving aminosalicylates (69%), corticosteroids (59%) and/or azathioprine or 6-MP (37%) at baseline. In both studies, 92% of patients received at least one of these medications.

Induction of clinical remission (defined as Mayo score ≤ 2 with no individual subscores > 1) at Week 8 was evaluated in both studies. Clinical remission at Week 52 and sustained clinical remission (defined as clinical remission at both Weeks 8 and 52) were evaluated in Study UC-II.

In Study UC-I, 390 TNF-blocker naïve patients were randomized to one of three treatment groups for the primary efficacy analysis. The placebo group received placebo at Weeks 0, 2, 4 and 6. The 160/80 group received 160 mg adalimumab at Week 0 and 80 mg at Week 2, and the 80/40 group received 80 mg adalimumab at Week 0 and 40 mg at Week 2. After Week 2, patients in both adalimumab treatment groups received 40 mg every other week.

In Study UC-II, 518 patients were randomized to receive either adalimumab 160 mg at Week 0, 80 mg at Week 2, and 40 mg every other week starting at Week 4 through Week 50, or placebo starting at Week 0 and every other week through Week 50. Corticosteroid taper was permitted starting at Week 8.

In both Studies UC-I and UC-II, a greater percentage of the patients treated with 160/80 mg of adalimumab compared to patients treated with placebo achieved induction of clinical remission. In Study UC-II, a greater percentage of the patients treated with 160/80 mg of adalimumab compared to patients treated with placebo achieved sustained clinical remission (clinical remission at both Weeks 8 and 52) (Table 15).

Table 15. Induction of Clinical Remission in Studies UC-I and UC-II and Sustained Clinical Remission in Study UC-II (Percent of Patients)
 | Study UC-I |  |  | Study UC-II
 | Placebo; N=130 | Adalimumab; 160/80; mg; N=130 | Treatment; Difference; (95% CI) | Placebo; N=246 | Adalimumab 160/80; mg; N=248 | Treatment; Difference; (95% CI)
Induction of Clinical; Remission (Clinical; Remission at Week 8) | 9.2% | 18.5% | 9.3%; (0.9%, 17.6%) | 9.3% | 16.5% | 7.2% [p<0.05 for adalimumab vs. placebo pairwise comparison of proportions]; (1.2%, 12.9%)
Sustained Clinical; Remission (Clinical; Remission at both Weeks 8 and 52) | N/A | N/A | N/A | 4.1% | 8.5% | 4.4%; (0.1%, 8.6%)
Clinical remission is defined as Mayo score ≤ 2 with no individual subscores > 1.
CI=Confidence interval

In Study UC-I, there was no statistically significant difference in clinical remission observed between the adalimumab 80/40 mg group and the placebo group at Week 8.

In Study UC-II, 17.3% (43/248) in the adalimumab group were in clinical remission at Week 52 compared to 8.5% (21/246) in the placebo group (treatment difference: 8.8%; 95% confidence interval (CI): [2.8%, 14.5%]; p<0.05).

In the subgroup of patients in Study UC-II with prior TNF-blocker use, the treatment difference for induction of clinical remission appeared to be lower than that seen in the whole study population, and the treatment differences for sustained clinical remission and clinical remission at Week 52 appeared to be similar to those seen in the whole study population. The subgroup of patients with prior TNF-blocker use achieved induction of clinical remission at 9% (9/98) in the adalimumab group versus 7% (7/101) in the placebo group, and sustained clinical remission at 5% (5/98) in the adalimumab group versus 1% (1/101) in the placebo group. In the subgroup of patients with prior TNF-blocker use, 10% (10/98) were in clinical remission at Week 52 in the adalimumab group versus 3% (3/101) in the placebo group.

14.9 Plaque Psoriasis

The safety and efficacy of adalimumab were assessed in randomized, double-blind, placebo-controlled studies in 1696 adult subjects with moderate to severe chronic plaque psoriasis (Ps) who were candidates for systemic therapy or phototherapy.

Study Ps-I evaluated 1212 subjects with chronic Ps with ≥10% body surface area (BSA) involvement, Physician’s Global Assessment (PGA) of at least moderate disease severity, and Psoriasis Area and Severity Index (PASI) ≥12 within three treatment periods. In period A, subjects received placebo or adalimumab at an initial dose of 80 mg at Week 0 followed by a dose of 40 mg every other week starting at Week 1. After 16 weeks of therapy, subjects who achieved at least a PASI 75 response at Week 16, defined as a PASI score improvement of at least 75% relative to baseline, entered period B and received open-label 40 mg adalimumab every other week. After 17 weeks of open label therapy, subjects who maintained at least a PASI 75 response at Week 33 and were originally randomized to active therapy in period A were re-randomized in period C to receive 40 mg adalimumab every other week or placebo for an additional 19 weeks. Across all treatment groups the mean baseline PASI score was 19 and the baseline Physician’s Global Assessment score ranged from “moderate” (53%) to “severe” (41%) to “very severe” (6%).

Study Ps-II evaluated 99 subjects randomized to adalimumab and 48 subjects randomized to placebo with chronic plaque psoriasis with ≥10% BSA involvement and PASI ≥12. Subjects received placebo, or an initial dose of 80 mg adalimumab at Week 0 followed by 40 mg every other week starting at Week 1 for 16 weeks. Across all treatment groups the mean baseline PASI score was 21 and the baseline PGA score ranged from “moderate” (41%) to “severe” (51%) to “very severe” (8%).

Studies Ps-I and II evaluated the proportion of subjects who achieved “clear” or “minimal” disease on the 6-point PGA scale and the proportion of subjects who achieved a reduction in PASI score of at least 75% (PASI 75) from baseline at Week 16 (see Table 17 and 18).

Additionally, Study Ps-I evaluated the proportion of subjects who maintained a PGA of “clear” or “minimal” disease or a PASI 75 response after Week 33 and on or before Week 52.

Table 17. Efficacy Results at 16 Weeks in Study Ps-I Number of Subjects (%)
 | Adalimumab 40 mg every other week | Placebo
 | N = 814 | N = 398
PGA: Clear or minimal [Clear = no plaque elevation, no scale, plus or minus hyperpigmentation or diffuse pink or red coloration] | 506 (62%) | 17 (4%)
PASI 75 | 578 (71%) | 26 (7%)
Minimal = possible but difficult to ascertain whether there is slight elevation of plaque above normal skin, plus or minus surface dryness with some white coloration, plus or minus up to red coloration

Table 18. Efficacy Results at 16 Weeks in Study Ps-II Number of Subjects (%)
 | Adalimumab 40 mg every other week | Placebo
 | N = 99 | N = 48
PGA: Clear or minimal [Clear = no plaque elevation, no scale, plus or minus hyperpigmentation or diffuse pink or red coloration] | 70 (71%) | 5 (10%)
PASI 75 | 77 (78%) | 9 (19%)
Minimal = possible but difficult to ascertain whether there is slight elevation of plaque above normal skin, plus or minus surface dryness with some white coloration, plus or minus up to red coloration

Additionally, in Study Ps-I, subjects on adalimumab who maintained a PASI 75 were re-randomized to adalimumab (N = 250) or placebo (N = 240) at Week 33. After 52 weeks of treatment with adalimumab, more subjects on adalimumab maintained efficacy when compared to subjects who were re-randomized to placebo based on maintenance of PGA of “clear” or “minimal” disease (68% vs. 28%) or a PASI 75 (79% vs. 43%).

A total of 347 stable responders participated in a withdrawal and retreatment evaluation in an open-label extension study. Median time to relapse (decline to PGA “moderate” or worse) was approximately 5 months. During the withdrawal period, no subject experienced transformation to either pustular or erythrodermic psoriasis. A total of 178 subjects who relapsed re-initiated treatment with 80 mg of adalimumab, then 40 mg every other week beginning at week 1. At week 16, 69% (123/178) of subjects had a response of PGA “clear” or “minimal”.

A randomized, double-blind study (Study Ps-III) compared the efficacy and safety of adalimumab versus placebo in 217 adult subjects. Subjects in the study had to have chronic plaque psoriasis of at least moderate severity on the PGA scale, fingernail involvement of at least moderate severity on a 5-point Physician’s Global Assessment of Fingernail Psoriasis (PGA-F) scale, a Modified Nail Psoriasis Severity Index (mNAPSI) score for the target-fingernail of ≥ 8, and either a BSA involvement of at least 10% or a BSA involvement of at least 5% with a total mNAPSI score for all fingernails of ≥ 20. Subjects received an initial dose of 80 mg adalimumab followed by 40 mg every other week (starting one week after the initial dose) or placebo for 26 weeks followed by open-label adalimumab treatment for an additional 26 weeks. This study evaluated the proportion of subjects who achieved “clear” or “minimal” assessment with at least a 2-grade improvement on the PGA-F scale and the proportion of subjects who achieved at least a 75% improvement from baseline in the mNAPSI score (mNAPSI 75) at Week 26.

At Week 26, a higher proportion of subjects in the adalimumab group than in the placebo group achieved the PGA-F endpoint. Furthermore, a higher proportion of subjects in the adalimumab group than in the placebo group achieved mNAPSI 75 at Week 26 (see Table 19).

Table 19. Efficacy Results at 26 Weeks
Endpoint | Adalimumab 40 mg; every other week [Subjects received 80 mg of adalimumab at Week 0, followed by 40 mg every other week starting at Week 1.]; N=109 | Placebo; N=108
PGA-F: ≥2-grade improvement and; clear or minimal | 49% | 7%
mNAPSI 75 | 47% | 3%

Nail pain was also evaluated and improvement in nail pain was observed in Study Ps-III.

14.10 Hidradenitis Suppurativa

Two randomized, double-blind, placebo-controlled studies (Studies HS-I and II) evaluated the safety and efficacy of adalimumab in a total of 633 adult subjects with moderate to severe hidradenitis suppurativa (HS) with Hurley Stage II or III disease and with at least 3 abscesses or inflammatory nodules. In both studies, subjects received placebo or adalimumab at an initial dose of 160 mg at Week 0, 80 mg at Week 2, and 40 mg every week starting at Week 4 and continued through Week 11. Subjects used topical antiseptic wash daily. Concomitant oral antibiotic use was allowed in Study HS-II.

Both studies evaluated Hidradenitis Suppurativa Clinical Response (HiSCR) at Week 12. HiSCR was defined as at least a 50% reduction in total abscess and inflammatory nodule count with no increase in abscess count and no increase in draining fistula count relative to baseline (see Table 18). Reduction in HS-related skin pain was assessed using a Numeric Rating Scale in patients who entered the study with an initial baseline score of 3 or greater on a 11 point scale.

In both studies, a higher proportion of adalimumab- than placebo-treated subjects achieved HiSCR (see Table 20).

Table 20. Efficacy Results at 12 Weeks in Subjects with Moderate to Severe Hidradenitis Suppurativa
 | HS Study 1 |  | HS Study 2 [19.3% of subjects in Study HS-II continued baseline oral antibiotic therapy during the study.]
 | Placebo | Adalimumab 40 mg; Weekly | Placebo | Adalimumab 40 mg; Weekly
Hidradenitis Suppurativa Clinical Response (HiSCR) | N = 154; 40 (26%) | N = 153; 64 (42%) | N=163; 45 (28%) | N=163; 96 (59%)

In both studies, from Week 12 to Week 35 (Period B), subjects who had received adalimumab were re-randomized to 1 of 3 treatment groups (adalimumab 40 mg every week, adalimumab 40 mg every other week, or placebo). Subjects who had been randomized to placebo were assigned to receive adalimumab 40 mg every week (Study HS-I) or placebo (Study HS-II).

During Period B, flare of HS, defined as ≥25% increase from baseline in abscesses and inflammatory nodule counts and with a minimum of 2 additional lesions, was documented in 22 (22%) of the 100 subjects who were withdrawn from adalimumab treatment following the primary efficacy timepoint in two studies.

14.11 Adult Uveitis

The safety and efficacy of adalimumab were assessed in adult patients with non-infectious intermediate, posterior and panuveitis excluding patients with isolated anterior uveitis, in two randomized, double-masked, placebo-controlled studies (UV I and II). Patients received placebo or adalimumab at an initial dose of 80 mg followed by 40 mg every other week starting one week after the initial dose. The primary efficacy endpoint in both studies was ´time to treatment failure´.

Treatment failure was a multi-component outcome defined as the development of new inflammatory chorioretinal and/or inflammatory retinal vascular lesions, an increase in anterior chamber (AC) cell grade or vitreous haze (VH) grade or a decrease in best corrected visual acuity (BCVA).

Study UV I evaluated 217 patients with active uveitis while being treated with corticosteroids (oral prednisone at a dose of 10 to 60 mg/day). All patients received a standardized dose of prednisone 60 mg/day at study entry followed by a mandatory taper schedule, with complete corticosteroid discontinuation by Week 15.

Study UV II evaluated 226 patients with inactive uveitis while being treated with corticosteroids (oral prednisone 10 to 35 mg/day) at baseline to control their disease. Patients subsequently underwent a mandatory taper schedule, with complete corticosteroid discontinuation by Week 19.

Clinical Response

Results from both studies demonstrated statistically significant reduction of the risk of treatment failure in patients treated with adalimumab versus patients receiving placebo. In both studies, all components of the primary endpoint contributed cumulatively to the overall difference between adalimumab and placebo groups (Table 21).

Table 21. Time to Treatment Failure in Studies UV I and UV II
 | UV I |  |  | UV II
 | Placebo; (N = 107) | Adalimumab; (N = 110) | HR; [95% CI] [HR of adalimumab versus placebo from proportional hazards regression with treatment as factor.] | Placebo; (N = 111) | Adalimumab; (N = 115) | HR; [95% CI]
Failure [Treatment failure at or after Week 6 in Study UV I, or at or after Week 2 in Study UV II, was counted as event. Subjects who discontinued the study were censored at the time of dropping out.] n (%) | 84 (78.5) | 60 (54.5) | 0.50; [0.36, 0.70] | 61 (55.0) | 45 (39.1) | 0.57; [0.39, 0.84]
Median Time to Failure (Months); [95% CI] | 3.0; [2.7, 3.7] | 5.6; [3.9, 9.2] | N/A | 8.3; [4.8, 12.0] | NE [NE = not estimable. Fewer than half of at-risk subjects had an event.] | N/A

Figure 3: Kaplan-Meier Curves Summarizing Time to Treatment Failure on or after Week 6 (Study UV I) or Week 2 (Study UV II)

[A1]To Applicant: updated the figures to align with he correct study.

Note: P# = Placebo (Number of Events/Number at Risk); A# = Adalimumab (Number of Events/Number at Risk).

15 REFERENCES

1. National Cancer Institute. Surveillance, Epidemiology, and End Results Database (SEER) Program. SEER Incidence Crude Rates, 17 Registries, 2000-2007.

16 HOW SUPPLIED/STORAGE AND HANDLING

HULIO® (adalimumab-fkjp) injection is supplied as a preservative-free, sterile, clear to slightly opalescent and colorless to pale brownish-yellow solution for subcutaneous administration. The following packaging configurations are available:

HULIO Prefilled Syringe Carton - 20 mg/0.4 mL

HULIO is supplied in a carton containing two alcohol preps and two dose trays. Each dose tray consists of a single-dose, 1 mL pre-filled plastic syringe with a fixed 29 gauge thin wall, ½ inch needle, providing 20 mg/0.4 mL of HULIO. The NDC number is 83257-016-42.

HULIO Prefilled Syringe Carton - 40 mg/0.8 mL

HULIO is supplied in a carton containing two alcohol preps and two dose trays. Each dose tray consists of a single-dose, 1 mL pre-filled plastic syringe with a fixed 29 gauge thin wall, ½ inch needle, providing 40 mg/0.8 mL of HULIO. The NDC number is 83257-017-42.

HULIO Prefilled Pen Carton - 40 mg/0.8 mL

HULIO is supplied in a carton containing two alcohol preps and two dose trays. Each dose tray consists of a single-dose pen, containing a 1 mL prefilled plastic syringe with a fixed 29 gauge thin wall, ½ inch needle, providing 40 mg/0.8 mL of HULIO. The NDC number is 83257-019-32.

Storage and Stability

Do not use beyond the expiration date on the container. HULIO must be refrigerated at 36°F to 46°F (2°C to 8°C). DO NOT FREEZE. Do not use if frozen even if it has been thawed.

Store in original carton until time of administration to protect from light.

If needed, for example when traveling, HULIO may be stored at room temperature up to a maximum of 77°F (25°C) for a period of up to 14 days, with protection from light. HULIO should be discarded if not used within the 14-day period. Record the date when HULIO is first removed from the refrigerator in the spaces provided on the carton and dose tray.

Do not store HULIO in extreme heat or cold.

17 PATIENT COUNSELING INFORMATION

Advise the patient or caregiver to read the FDA-approved patient labeling (Medication Guide and Instructions for Use).

Infections

Inform patients that HULIO may lower the ability of their immune system to fight infections. Instruct patients of the importance of contacting their healthcare provider if they develop any symptoms of infection, including tuberculosis, invasive fungal infections, and reactivation of hepatitis B virus infections [see Warnings and Precautions (5.1, 5.2, 5.4)].

Malignancies

Counsel patients about the risk of malignancies while receiving HULIO [see Warnings and Precautions (5.2)].

Hypersensitivity Reactions

Advise patients to seek immediate medical attention if they experience any symptoms of severe hypersensitivity reactions.

Other Medical Conditions

Advise patients to report any signs of new or worsening medical conditions such as congestive heart failure, neurological disease, autoimmune disorders, or cytopenias. Advise patients to report any symptoms suggestive of a cytopenia such as bruising, bleeding, or persistent fever [see Warnings and Precautions (5.5, 5.6, 5.8, 5.9)].

Instructions on Injection Technique

Inform patients that the first injection is to be performed under the supervision of a qualified health care professional. If a patient or caregiver is to administer HULIO, instruct them in injection techniques and assess their ability to inject subcutaneously to ensure the proper administration of HULIO [see Instructions for Use].

For patients who will use the HULIO Pen, tell them that they:

- Will hear two "clicks" during the Hulio injection. The first ‘click’ means the start of injection and second ‘click’ means the end of injection.
- To start injection, push the Pen body down. Continue holding down after hearing the first ‘click’.
- In the viewing window, the orange indicator will advance to show the progress of the injection.
- When injection has finished, there will be a second ‘click’ and the ‘Orange Indicator’ will completely block the viewing window.

Instruct patients to dispose of their used needles and syringes or used Pen in an FDA-cleared sharps disposal container immediately after use. Instruct patients not to dispose of loose needles and syringes or Pen in their household trash. Instruct patients that if they do not have an FDA-cleared sharps disposal container, they may use a household container that is made of a heavy-duty plastic, can be closed with a tight-fitting and puncture-resistant lid without sharps being able to come out, upright and stable during use, leak-resistant, and properly labeled to warn of hazardous waste inside the container.

Instruct patients that when their sharps disposal container is almost full, they will need to follow their community guidelines for the correct way to dispose of their sharps disposal container. Instruct patients that there may be state or local laws regarding disposal of used needles and syringes. Refer patients to the FDA’s website at http://www.fda.gov/safesharpsdisposal for more information about safe sharps disposal, and for specific information about sharps disposal in the state that they live in.

Instruct patients not to dispose of their used sharps disposal container in their household trash unless their community guidelines permit this. Instruct patients not to recycle their used sharps disposal container.

MEDICATION GUIDE

HULIO®(hue lee oh)
(adalimumab-fkjp)
injection, for subcutaneous use

Read the Medication Guide that comes with HULIO before you start taking it and each time you get a refill. There may be new information. This Medication Guide does not take the place of talking with your healthcare provider about your medical condition or treatment.

What is the most important information I should know about HULIO?

HULIO is a medicine that affects your immune system. HULIO can lower the ability of your immune system to fight infections. Serious infections have happened in people taking adalimumab products. These serious infections include tuberculosis (TB) and infections caused by viruses, fungi or bacteria that have spread throughout the body. Some people have died from these infections.

- Your healthcare provider should test you for TB before starting HULIO.
- Your healthcare provider should check you closely for signs and symptoms of TB during treatment with HULIO.

You should not start taking HULIO if you have any kind of infection unless your healthcare provider says it is okay.

Before starting HULIO, tell your healthcare provider if you:

- think you have an infection or have symptoms of an infection such as:

- fever, sweats, or chills
- muscle aches
- cough
- shortness of breath
- blood in phlegm

- warm, red, or painful skin or sores on your body
- diarrhea or stomach pain
- burning when you urinate or urinate more often than normal
- feel very tired
- weight loss

- are being treated for an infection
- get a lot of infections or have infections that keep coming back
- have diabetes
- have TB, or have been in close contact with someone with TB
- were born in, lived in, or traveled to countries where there is more risk for getting TB. Ask your healthcare provider if you are not sure.
- live or have lived in certain parts of the country (such as the Ohio and Mississippi River valleys) where there is an increased risk for getting certain kinds of fungal infections (histoplasmosis, coccidioidomycosis, or blastomycosis). These infections may happen or become more severe if you use HULIO. Ask your healthcare provider if you do not know if you have lived in an area where these infections are common.
- have or have had hepatitis B
- use the medicine ORENCIA (abatacept), KINERET (anakinra), RITUXAN (rituximab), IMURAN (azathioprine), or PURINETHOL (6–mercaptopurine, 6-MP).
- are scheduled to have major surgery

After starting HULIO, call your healthcare provider right away if you have an infection, or any sign of an infection.

HULIO can make you more likely to get infections or make any infection that you may have worse.

Cancer

- For children and adults taking Tumor Necrosis Factor (TNF)-blockers, including HULIO, the chances of getting cancer may increase.
- There have been cases of unusual cancers in children, teenagers, and young adults using TNF-blockers.
- People with rheumatoid arthritis (RA), especially more serious RA, may have a higher chance for getting a kind of cancer called lymphoma.
- If you use TNF blockers including HULIO your chance of getting two types of skin cancer may increase (basal cell cancer and squamous cell cancer of the skin). These types of cancer are generally not life-threatening if treated. Tell your healthcare provider if you have a bump or open sore that does not heal.
- Some people receiving TNF blockers including HULIO developed a rare type of cancer called hepatosplenic T-cell lymphoma. This type of cancer often results in death. Most of these people were male teenagers or young men. Also, most people were being treated for Crohn’s disease or ulcerative colitis with another medicine called IMURAN (azathioprine) or PURINETHOL (6-mercaptopurine, 6–MP).

What is HULIO?

HULIO is a medicine called a Tumor Necrosis Factor (TNF) blocker. HULIO is used:

- To reduce the signs and symptoms of:
  - moderate to severe RA in adults. HULIO can be used alone, with methotrexate, or with certain other medicines.
  - moderate to severe polyarticular juvenile idiopathic arthritis (JIA) in children 2 years and older. HULIO can be used alone or with methotrexate.
  - psoriatic arthritis (PsA) in adults. HULIO can be used alone or with certain other medicines.
  - ankylosing spondylitis (AS) in adults.
  - moderate to severe hidradenitis suppurativa (HS) in adults.

- To treat moderate to severe Crohn’s disease (CD) in adults and children 6 years of age and older.
- To treat moderate to severe ulcerative colitis (UC) in adults.
  It is not known if adalimumab products are effective in people who stopped responding to or could not tolerate TNF-blocker medicines.
- To treat moderate to severe chronic (lasting a long time) plaque psoriasis (Ps) in adults who have the condition in many areas of their body and who may benefit from taking injections or pills (systemic therapy) or phototherapy (treatment using ultraviolet light alone or with pills).
- To treat non-infectious intermediate, posterior, and panuveitis in adults.

What should I tell my healthcare provider before taking HULIO?

HULIO may not be right for you. Before starting HULIO, tell your healthcare provider about all of your medical conditions, including if you:

- have an infection. See “What is the most important information I should know about HULIO?”
- have or have had cancer.
- have any numbness or tingling or have a disease that affects your nervous system such as multiple sclerosis or Guillain-Barré syndrome.
- have or had heart failure.
- have recently received or are scheduled to receive a vaccine. You may receive vaccines, except for live vaccines while using HULIO. Children should be brought up to date with all vaccines before starting HULIO.
- are allergic to HULIO or to any of its ingredients. See the end of this Medication Guide for a list of ingredients in HULIO.
- are pregnant or plan to become pregnant, breastfeeding or plan to breastfeed. You and your healthcare provider should decide if you should take HULIO while you are pregnant or breastfeeding.
- have a baby and you were using HULIO during your pregnancy. Tell your baby’s healthcare provider before your baby receives any vaccines.

Tell your healthcare provider about all the medicines you take, including prescription and over-the-counter medicines, vitamins, and herbal supplements.

Especially tell your healthcare provider if you use:

- ORENCIA (abatacept), KINERET (anakinra), REMICADE (infliximab), ENBREL (etanercept), CIMZIA (certolizumab pegol) or SIMPONI (golimumab), because you should not use HULIO while you are also using one of these medicines.
- RITUXAN (rituximab). Your healthcare provider may not want to give you HULIO if you have received RITUXAN (rituximab) recently.
- IMURAN (azathioprine) or PURINETHOL (6–mercaptopurine, 6-MP).

Keep a list of your medicines with you to show your healthcare provider and pharmacist each time you get a new medicine.

How should I take HULIO?

- HULIO is given by an injection under the skin. Your healthcare provider will tell you how often to take an injection of HULIO. This is based on your condition to be treated. Do not inject HULIO more often than you were prescribed.
- See the Instructions for Use inside the carton for complete instructions for the right way to prepare and inject HULIO.
- Make sure you have been shown how to inject HULIO before you do it yourself. You can call your healthcare provider or 1-800-796-9526 if you have any questions about giving yourself an injection. Someone you know can also help you with your injection after they have been shown how to prepare and inject HULIO.
- Do not try to inject HULIO yourself until you have been shown the right way to give the injections. If your healthcare provider decides that you or a caregiver may be able to give your injections of HULIO at home, you should receive training on the right way to prepare and inject HULIO.
- Do not miss any doses of HULIO unless your healthcare provider says it is okay. If you forget to take HULIO, inject a dose as soon as you remember. Then, take your next dose at your regular scheduled time. This will put you back on schedule. In case you are not sure when to inject HULIO, call your healthcare provider or pharmacist.
- If you take more HULIO than you were told to take, call your healthcare provider.

What are the possible side effects of HULIO?

HULIO can cause serious side effects, including:

See “What is the most important information I should know about HULIO?”

- Serious Infections.
  Your healthcare provider will examine you for TB and perform a test to see if you have TB. If your healthcare provider feels that you are at risk for TB, you may be treated with medicine for TB before you begin treatment with HULIO and during treatment with HULIO. Even if your TB test is negative your healthcare provider should carefully monitor you for TB infections while you are taking HULIO. People who had a negative TB skin test before receiving adalimumab products have developed active TB. Tell your healthcare provider if you have any of the following symptoms while taking or after taking HULIO:

- cough that does not go away
- low grade fever

- weight loss
- loss of body fat and muscle (wasting)

- Hepatitis B infection in people who carry the virus in their blood.
  If you are a carrier of the hepatitis B virus (a virus that affects the liver), the virus can become active while you use HULIO. Your healthcare provider should do blood tests before you start treatment, while you are using HULIO, and for several months after you stop treatment with HULIO. Tell your healthcare provider if you have any of the following symptoms of a possible hepatitis B infection:

- muscle aches
- feel very tired
- dark urine
- skin or eyes look yellow
- little or no appetite
- vomiting

- clay-colored bowel movements
- fever
- chills
- stomach discomfort
- skin rash

- Allergic reactions. Allergic reactions can happen in people who use HULIO. Call your healthcare provider or get medical help right away if you have any of these symptoms of a serious allergic reaction:

- hives
- trouble breathing

- swelling of your face, eyes, lips or mouth

- Nervous system problems. Signs and symptoms of a nervous system problem include: numbness or tingling, problems with your vision, weakness in your arms or legs, and dizziness.
- Blood problems. Your body may not make enough of the blood cells that help fight infections or help to stop bleeding. Symptoms include a fever that does not go away, bruising or bleeding very easily, or looking very pale.
- New heart failure or worsening of heart failure you already have. Call your healthcare provider right away if you get new worsening symptoms of heart failure while taking HULIO, including:

- shortness of breath
- sudden weight gain

- swelling of your ankles or feet

- Immune reactions including a lupus-like syndrome. Symptoms include chest discomfort or pain that does not go away, shortness of breath, joint pain, or a rash on your cheeks or arms that gets worse in the sun. Symptoms may improve when you stop HULIO.
- Liver problems. Liver problems can happen in people who use TNF-blocker medicines.
  These problems can lead to liver failure and death. Call your healthcare provider right away if you have any of these symptoms:

- feel very tired
- poor appetite or vomiting

- skin or eyes look yellow
- pain on the right side of your stomach (abdomen)

- Psoriasis. Some people using adalimumab products had new psoriasis or worsening of psoriasis they already had. Tell your healthcare provider if you develop red scaly patches or raised bumps that are filled with pus. Your healthcare provider may decide to stop your treatment with HULIO.

Call your healthcare provider or get medical care right away if you develop any of the above symptoms. Your treatment with HULIO may be stopped.

The most common side effects of HULIO include:

- injection site reactions: redness, rash, swelling, itching, or bruising. These symptoms usually will go away within a few days. Call your healthcare provider right away if you have pain, redness or swelling around the injection site that does not go away within a few days or gets worse.
- upper respiratory infections (including sinus infections).
- headaches.
- rash.

These are not all the possible side effects with HULIO. Tell your healthcare provider if you have any side effect that bothers you or that does not go away. Ask your healthcare provider or pharmacist for more information.

Call your doctor for medical advice about side effects. You may report side effects to FDA at 1-800-FDA-1088.

How should I store HULIO?

- Store HULIO in the refrigerator at 36ºF to 46ºF (2ºC to 8ºC). Store HULIO in the original carton until use to protect it from light.
- Do not freeze HULIO. Do not use HULIO if frozen, even if it has been thawed.
- Refrigerated HULIO may be used until the expiration date printed on the HULIO carton, dose tray, Pen or prefilled syringe. Do not use HULIO after the expiration date.
- If needed, for example when you are traveling, you may also store HULIO at room temperature up to 77°F (25°C) for up to 14 days. Store HULIO in the original carton until use to protect it from light.
- Throw away HULIO if it has been kept at room temperature and not been used within 14 days.
- Record the date you first remove HULIO from the refrigerator in the spaces provided on the carton and dose tray.
- Do not store HULIO in extreme heat or cold.
- Do not use a Pen or prefilled syringe if the liquid is cloudy, discolored, or has flakes or particles in it.

Keep HULIO, injection supplies, and all other medicines out of the reach of children.

General information about the safe and effective use of HULIO.

Medicines are sometimes prescribed for purposes other than those listed in a Medication

Guide. Do not use HULIO for a condition for which it was not prescribed. Do not give

HULIO to other people, even if they have the same condition. It may harm them.

This Medication Guide summarizes the most important information about HULIO. If you

would like more information, talk with your healthcare provider. You can ask your pharmacist or healthcare provider for information about HULIO that is written for health professionals.

What are the ingredients in HULIO?

Active ingredient: adalimumab-fkjp

HULIO Pen 40 mg/0.8 mL, HULIO 40 mg/0.8 mL prefilled syringe, HULIO 20 mg/0.4 mL prefilled syringe.

Inactive ingredients: methionine, monosodium glutamate, polysorbate 80, sorbitol and Water for Injection. Hydrochloric acid is added as necessary to adjust pH.

Manufactured by: Biocon Biologics Inc, 245 Main St, 2nd Floor, Cambridge, MA 02142, U.S.A.

Product of Japan

U.S. License Number 2324

For more information, call Biocon Biologics at 1-833-986-1468 or you can enroll in a patient support program by calling 1-833-44-HULIO (1-833-444-8546).

This Medication Guide has been approved by the U.S. Food and Drug Administration. Revised: 02/2025

INSTRUCTIONS FOR USE - Pen

HULIO® Pen (hue lee oh)

(adalimumab-fkjp) injection

40 mg/0.8 mL

Single-Dose Pen

Important Information:

- Do not try to inject HULIO yourself until you have been shown the right way to give the injections and have read and understand this Instructions for Use.
- If your healthcare provider decides that you or a caregiver may be able to give your injections of HULIO at home, you should receive training on the right way to prepare and inject HULIO.
- There will be a “click” during your injections. You should practice injecting HULIO with your healthcare provider so that you are not startled by this “click” when you start giving yourself injections at home.
- It is important that you read, understand, and follow these instructions so that you inject HULIO the right way. It is also important to talk to your healthcare provider to be sure you understand your HULIO dosing instructions.
- To help you remember when to inject HULIO, you can mark your calendar ahead of time.
- Call your healthcare provider if you or your caregiver have any questions about the right way to inject HULIO.
- Each HULIO Pen can only be used one time. Throw the used Pen away (See How should I throw away (dispose of) the used HULIO Pen) after one dose, even if there is still medicine left in it. Do not reuse your HULIO Pen.

For Questions or Assistance, Call Biocon Biologics at 1-833-986-1468

The figure below shows what the HULIO Pen looks like. See Figure A.

Step 1. Gather the Supplies for Your Injection

- Take your HULIO Pen out of the refrigerator 15 to 30 minutes before injecting to allow the liquid to reach room temperature.
  - Do not warm HULIO in any other way (for example, do not warm it in a microwave or in hot water).
  - Do not use HULIO if it has been frozen, even if it has been thawed.
  - Do not put the HULIO Pen back in the refrigerator after reaching room temperature.

- Do not uncap your HULIO Pen until you are ready to inject and will not be interrupted.

You will need the following supplies for each injection of HULIO.

- 1 HULIO Pen (See Figure A)
- 1 alcohol swab
- 1 cotton ball or gauze pad (not included in your HULIO carton)
- Puncture-resistant sharps disposal container for HULIO Pen disposal (not included in your HULIO carton). See the “How should I throw away (dispose of) the used HULIO PEN?” section at the end of this Instructions for Use.

If you do not have all the supplies you need to give yourself an injection, go to a pharmacy or call your pharmacist.

Find a clean, flat surface to place the supplies on.

Step 2. Check the Carton, Dose Tray and HULIO Pen

- Make sure the name HULIO appears on the carton, dose tray, and HULIO Pen label.
- Check the seals on the top or bottom of the carton to make sure they are not broken or missing.
- Check the expiration date on the carton, dose tray, and HULIO Pen.
- Do not usethe HULIO Pen and call your healthcare provider or pharmacist if:
  - you drop or crush your HULIO Pen.
  - the seals on the top or bottom of the carton are broken or missing.
  - the expiration date on the carton, dose tray, and Pen has passed.
  - The HULIO PEN has been frozen or left in direct sunlight.
  - HULIO has been kept at room temperature for longer than 14 days or HULIO has been stored above 77°F (25°C).
  - the liquid in the HULIO Pen is cloudy, discolored or has flakes or particles in it.

See the “How should I store HULIO?” section at the end of this Instructions for Use.

Check the fluid level in the Pen:

- Hold the Pen with the protective clear cap covering the orange activator pointed down. (See Figure B).
- Make sure the amount of liquid in the Pen is at the fill line or close to the fill line seen through the window. You may need to shake gently to see the liquid. This is the full dose of HULIO that you will inject. (See Figure B).
- If the Pen does not have the full amount of liquid, do not use that Pen. Call your pharmacist.

- Turn the Pen and hold with the protective clear cap covering the orange activator pointed sideways. (See Figure C).

- Check the solution through the windows on the side of the Pen to make sure the liquid is clear and colorless to pale brownish-yellow.
- Do not use your HULIO Pen if the liquid is cloudy, discolored, or if it has flakes or particles in it. Call your pharmacist.
- It is normal to see one or more bubbles in the window.

Step 3. Choose the Injection Site

- Wash your hands with soap and water and dry well.
- Choose an injection site on:
  - the front of your thighs or
  - your lower abdomen (belly). If you choose your abdomen, do not use the area 2 inches around your belly button (navel). (See Figure D).
- Choose a different site (rotate) each time you give yourself an injection. Each new injection should be given at least 1 inch from a site you used before.
- Do not inject HULIO into skin that is:
  - sore (tender)
  - bruised
  - red
  - hard
  - Scarred or where you have stretch marks
- If you have psoriasis, do not inject directly into any raised, thick, red or scaly skin patches or lesions on your skin.
- Do not inject through your clothes.

Figure D

Step 4: Prepare the Injection Site

- Wipe the injection site with an alcohol prep (swab) using a circular motion.
- Do not touch this area again before giving the injection.
- Allow the skin to dry before injecting. Do not fan or blow on the clean area.

Step 5. Prepare the HULIO PEN

- Do not remove the protective clear cap until right before your injection.
- Hold the middle of the Pen (white body) with one hand so that you are not touching the protective clear cap. Turn the Pen so that the orange activator end is pointing down. See (Figure E).

- With your other hand, pull the protective clear cap straight off (do not twist the cap). Make sure the small needle cover of the syringe has come off with the protective clear cap. (See Figure F).

- Important: Do not put the protective clear cap back on. It may damage the needle.
- Throw away the protective clear cap.
- The orange activator which covers the needle is where the needle comes out. The needle can now be seen.
- Caution:
  - Never put your thumb, fingers, or hand over the orange activator after the protective clear cap is removed.
  - Never press or push the orange activator with your thumb, fingers, or hand.
  - If accidental injection to your fingers or hands happens, apply first-aid and either call your healthcare provider or go to the nearest hospital emergency room if needed.
  - Do not touch the needle with your fingers or let the needle touch anything.
- You may see a few drops of liquid come out of the needle. This is normal.
- Turn the Pen so the white end is pointed up. (See Figure G).

- Hold the Pen so that you can see the window. (See Figure H). It is normal to see one or more bubbles in the window.

Step 6. Position the Pen

- Squeeze the area of the cleaned skin and hold it firmly until the injection is complete. (See Figure I). You will inject into this raised area of skin.

- Place the orange activator end of the Pen straight (at a 90º angle) and flat against the raised area of your skin that you are squeezing.
- Place the Pen so that it will not inject the needle into your fingers that are holding the raised skin. (See Figure J).

Step 7. Inject HULIO

- It is important that you firmly push the Pen down all the way against the injection site to begin the injection. Try not to cover the window. (See Figure K).
- Do not move, twist, or rotate the Pen during the injection.

- Keep pushing down to prevent the Pen from moving away from the skin during the injection.
- You will hear a loud ‘click’ when the orange activator is pressed down against the injection site. The loud click means the start of the injection.
- Continue to push the Pen against your squeezed, raised skin until all the medicine is injected. This can take up to 10 seconds, so count slowly to ten. Keep pushing the Pen against the squeezed, raised skin of your injection site for the whole time so you get the full dose of medicine.
- You will know that the injection has finished when:
- A 2nd ‘Click’ was heard, and
- Orange indicator has stopped moving and completely blocked the viewing window (See Figure L)
- 10 seconds has passed.
- Make sure all 3 of these have happened to make certain all the medicine was delivered. If the needle did not retract or you do not think you received the full dose, contact your healthcare provider for help.

- When the injection is finished, slowly pull the Pen from your skin. The white needle sleeve will move to cover the needle tip. (See Figure M).

- Do not touch the needle. The white needle sleeve is there to prevent you from touching the needle.
- If the needle did not retract or you do not think you received the full dose, contact your healthcare provider for help.
- There may be a small amount of liquid on the injection site. This is normal.
- Press a cotton ball or gauze pad over the injection site and hold it for 10 seconds. Do not rub the injection site. You may have slight bleeding. This is normal.

Step 8. Throw away (dispose of) your used HULIO Pen in a sharps disposal container right away after use. See the section “How should I throw away (dispose of) the used HULIO Pen?”

How should I throw away (dispose of) the used HULIO PEN?

- Put your Pen in an FDA-cleared sharps disposal container right away after use. (See Figure N). Do not throw away the Pen in your household trash.
- Do not try to touch the needle. The orange needle sleeve is there to prevent you from touching the needle.

- If you do not have a FDA-cleared sharps disposal container, you may use a household container that is:
  - made of a heavy-duty plastic,
  - Can be closed with a tight-fitting, puncture-resistant lid, without sharps being able to come out,
  - upright and stable during use,
  - leak-resistant, and properly labeled to warn of hazardous waste inside the container.
- When your sharps disposal container is almost full, you will need to follow your community guidelines for the right way to dispose of your sharps disposal container. There may be state or local laws about how you should throw away used needles and syringes. For more information about safe sharps disposal, and for specific information about sharps disposal in the state that you live in, go to the FDA’s website at: http://www.fda.gov/safesharpsdisposal.
- For the safety and health of you and others, never re-use your HULIO Pens.
- The used alcohol pads, cotton balls, dose trays and packaging may be placed in your household trash.
- Do not dispose of your used sharps disposal container in your household trash unless your community guidelines permit this. Do not recycle your used sharps disposal container.
- Always keep the sharps container out of the reach of children.

Keep a record of the dates and location of your injection sites. To help you remember when to take HULIO, you can mark your calendar ahead of time.

How should I Store HULIO?

- Store HULIO in the refrigerator between 36ºF to 46ºF (2ºC to 8ºC).
- Store HULIO in the original carton until use to protect it from light.
- Do not freeze HULIO.
- If needed, for example when you are traveling, you may also store HULIO at room temperature up to 77°F (25°C) for up to 14 days.
- Throw away HULIO if it has been kept at room temperature and not been used within 14 days.
- Do not store HULIO in extreme heat or cold, such as a hot car, or a freezing car overnight.
- Keep HULIO, injection supplies, and all other medicines out of the reach of children.

Manufactured by and for:

Biocon Biologics Inc.

245 Main St, 2nd Floor,

Cambridge, MA 02142, U.S.A.

U.S. License No. 2324

Product of Japan

This Instructions for Use has been approved by the U.S. Food and Drug Administration.

Issued: 02/2025

INSTRUCTIONS FOR USE - Syringe

HULIO® (hueꞌ lee oh)

(adalimumab-fkjp) injection

40 mg/0.8 mL and 20 mg/0.4 mL

Single-Dose Prefilled Syringe

Important Information:

- Do not try to inject HULIO yourself until you have been shown the right way to give the injections and have read and understand this Instructions for Use.
- If your healthcare provider decides that you or a caregiver may be able to give your injections of HULIO at home, you should receive training on the right way to prepare and inject HULIO.
- It is important that you read, understand, and follow these instructions so that you inject HULIO the right way. It is also important to talk to your healthcare provider to be sure you understand your HULIO dosing instructions.
- To help you remember when to inject HULIO, you can mark your calendar ahead of time.
- Call your healthcare provider if you or your caregiver have any questions about the right way to inject HULIO.
- Each HULIO Prefilled Syringe can only be used one time. Throw the used Prefilled Syringe away (See How should I throw away (dispose of) the used Prefilled Syringe?) after one dose, even if there is still medicine left in it. Do not reuse your HULIO Prefilled Syringe.

For Questions or Assistance, Call Biocon Biologics at 1-833-986-1468

The figure shows what a prefilled syringe looks like. See Figure A.

Step 1. Gather the Supplies for Your Injection

- Take your HULIO prefilled syringe out of the refrigerator 15 to 30 minutes before injecting to allow the liquid to reach room temperature.
  - Do not warm HULIO in any other way (for example, do not warm it in a microwave or in hot water).
  - Do not use HULIO if it has been frozen, even if it has been thawed.
  - Do not put HULIO back in the refrigerator after reaching room temperature.
- Do not uncap your HULIO Prefilled Syringe until you are ready to inject and will not be interrupted.

You will need the following supplies for each injection of HULIO.

- 1 HULIO Prefilled Syringe (See Figure A)
- 1 alcohol swab
- 1 cotton ball or gauze pad (not included in your HULIO carton)
- Puncture-resistant sharps disposal container for HULIO prefilled syringe disposal (not included in your HULIO carton). See “How should I throw away (dispose of) the used prefilled syringes and needles?” section at the end of this Instructions for Use.

If you do not have all the supplies you need to give yourself an injection, go to a pharmacy or call your pharmacist.

Find a clean, flat surface to place the supplies on.

Step 2. Check the carton, dose tray, and prefilled Syringe

- Make sure the name HULIO appears on the dose tray and prefilled syringe label.
- Check the seals on the top or bottom of the carton to make sure they are not broken or missing.
- Check the expiration date on the carton, dose tray, and HULIO Prefilled Syringe.

- Do not use the HULIO Prefilled Syringe and call your healthcare provider or pharmacist if:

o you drop or crush your HULIO Prefilled Syringe.

o the seals on the top or bottom of the carton are broken or missing.

o the expiration date on the carton, dose tray, and HULIO Prefilled Syringe have passed.

o the prefilled syringe has been frozen or left in direct sunlight.

o HULIO has been kept at room temperature for longer than 14 days or HULIO has been

stored above 77°F (25°C).

o the liquid in the prefilled syringe is cloudy, discolored or has flakes or particles in it.

See the “How should I store HULIO?” section at the end of this Instructions for Use.

Check the fluid level in the syringe:

- Hold the syringe with the covered needle pointing down. (See Figure B).

- Hold the syringe at eye level. Look closely to make sure that the amount of liquid in the syringe is the same or close to the:
- 0.8 mL line for the 40 mg prefilled syringe. (See Figure C).
- 0.4 mL line for the 20 mg prefilled syringe. (See Figure C).

- You may need to shake gently to see liquid.
- The top of the liquid may be curved. If the syringe does not have the correct amount of liquid, do not use that syringe. Call your pharmacist.

Step 3. Choose the Injection Site

- Wash your hands with soap and water and dry well.
- Choose an injection site on:
- the front of your thighs or
- your lower abdomen (belly). If you choose your abdomen, do not use the area 2 inches around your belly button (navel). (See Figure D).
- Choose a different site (rotate) each time you give yourself an injection. Each new injection should be given at least 1 inch from a site you used before.
- Do not inject HULIO into skin that is:
- sore (tender)
- bruised
- red
- hard
- scarred or where you have stretch marks
- If you have psoriasis, do not inject directly into any raised, thick, red or scaly skin patches or lesions on your skin.
- Do not inject through your clothes.

Step 4. Prepare the Injection Site

- Wipe the injection site with an alcohol prep (swab) using a circular motion.
- Do not touch this area again before giving the injection.
- Allow the skin to dry before injecting. Do not fan or blow on the clean area.

Step 5. Prepare the HULIO Prefilled Syringe and Needle

- Do not remove the needle cover until right before your injection.
- Hold the syringe in one hand. With the other hand gently remove the needle cover. (See Figure E).
- Throw away the needle cover.

Important:

- Do not touch the needle with your fingers or let the needle touch anything.
- Do not replace the needle cover.
- Do not remove air bubble(s).
- Do not use the syringe if dropped after removing the needle cover.
- You may see a drop of liquid at the end of the needle. This is normal.

Step 6. Position the Syringe

- Hold the body of the prefilled syringe in one hand between the thumb and index finger. Hold the syringe in your hand like a pencil. (See Figure F).

- Do not pull back on the plunger at any time.
- With your other hand, gently squeeze the area of the cleaned skin and hold it firmly. (See Figure G).

Step 7. Inject HULIO

- Using a quick, dart-like motion, insert the needle into the squeezed skin at about a 45-degree angle. (See Figure H).

- After the needle is in, let go of the skin.
- Do not move, twist, or rotate the Syringe during the injection.
- Slowly push the plunger all the way in until all the liquid is injected and the syringe is empty.
- If the plunger is not pressed all the way down the Needle Safety Feature will not activate afterwards to cover the needle
- Do not move, twist, or rotate the syringe during injection.
- Pull the needle out of the skin while keeping the syringe at the same angle, then release your thumb from the plunger.
- The needle will retract and the Needle Safety Feature will cover the needle. (See Figure I).

Caution: If the needle did not retract or you do not think you received the full dose, contact your healthcare provider for help.

- Press a cotton ball or gauze pad over the injection site and hold it for 10 seconds. Do not rub the injection site. You may have slight bleeding. This is normal.

Step 8. Throw away (dispose of) your used HULIO Prefilled Syringe and needle in a sharps disposal container right away after use. (See Figure J). “How should I throw away (dispose of) used prefilled syringes and needles?”

How should I throw away (dispose of) used prefilled syringes and needles?

- Put your used needles and syringes in a FDA-cleared sharps disposal container right away after use. (See Figure J). Do not throw away (dispose of) loose needles and syringes in your household trash.
- Do not try to touch the needle.

- If you do not have a FDA-cleared sharps disposal container, you may use a household container that is:
- made of a heavy-duty plastic,
- can be closed with a tight-fitting, puncture-resistant lid, without sharps being able to come out,
- upright and stable during use,
- leak-resistant, and
- properly labeled to warn of hazardous waste inside the container.
- When your sharps disposal container is almost full, you will need to follow your community guidelines for the right way to dispose of your sharps disposal container. There may be state or local laws about how you should throw away used needles and syringes. For more information about safe sharps disposal, and for specific information about sharps disposal in the state that you live in, go to the FDA’s website at: http://www.fda.gov/safesharpsdisposal.
- For the safety and health of you and others, needles and used syringes must never be re-used.
- The used alcohol pads, cotton balls, dose trays and packaging may be placed in your household trash.
- Do not dispose of your used sharps disposal container in your household trash unless your community guidelines permit this. Do not recycle your used sharps disposal container.
- Always keep the sharps container out of the reach of children.

Keep a record of the dates and location of your injection sites in the injection diary. To help you remember when to take HULIO, you can mark your calendar ahead of time.

How should I store HULIO?

- Store HULIO in the refrigerator between 36ºF to 46ºF (2ºC to 8ºC).
- Store HULIO in the original carton until use to protect it from light.
- Do not freeze HULIO.
- If needed, for example when you are traveling, you may also store HULIO at room temperature up to 77°F (25°C) for up to 14 days. Store HULIO in the original carton until use to protect it from light.
- Throw away HULIO if it has been kept at room temperature and not been used within 14 days.
- Do not store HULIO in extreme heat or cold such as a hot car, or a freezing car overnight.
- Keep HULIO, injection supplies, and all other medicines out of the reach of children.

Manufactured by:

Biocon Biologics Inc.

245 Main St, 2nd Floor,

Cambridge, MA 02142, U.S.A.

U.S. License No. 2324

Product of Japan

Revised: 02/2025

This Instructions for Use has been approved by the U.S. Food and Drug Administration.

PRINCIPAL DISPLAY PANEL – 20 mg/0.4 mL Syringe

NDC 83257-016-42

Hulio®

(adalimumab-fkjp) injection

20 mg/0.4 mL Syringe

FOR SUBCUTANEOUS USE ONLY

ATTENTION PHARMACIST: Each patient is required to receive the enclosed Medication Guide.

The entire carton is to be dispensed as a unit.
Return to pharmacy if dose tray seal is broken or missing.

2 Single-Dose
Preﬁlled Syringes

29 Gauge Needle

This carton contains:

- 2 dose trays (each containing
  1 single-dose preﬁlled syringe
  with 29 gauge 1/2 inch length
  ﬁxed needle)
- 2 alcohol preps
- 1 Quick Reference Guide
- 1 Instructions for Use
- 1 Medication Guide
- 1 Prescribing Information

Rx only
Each 0.4 mL single-dose prefilled syringe contains 20 mg of
adalimumab-fkjp, methionine (0.30 mg), monosodium glutamate
(0.75 mg), polysorbate 80 (0.40 mg), sorbitol (19.1 mg) and Water for
Injection, USP. Hydrochloric acid is added as necessary to adjust pH.

Contains no preservatives.

Prefilled syringe is for one time use only.
Dosage: See Prescribing Information.
Do not use beyond the expiration date.
Store in carton until time of administration with
protection from light.
Store in refrigerator at 36°F to 46°F (2°C to 8°C).
A HULIO prefilled syringe may be stored at room
temperature up to a maximum of 77°F (25°C) for up to
14 days with protection from light.

DO NOT FREEZE.

Manufactured by:
Biocon Biologics Inc.
245 Main St, 2nd Floor
Cambridge,MA 02142, U.S.A
U.S. License No. 2324
Product of Japan

HULIO® is a registered trademark of Fujifilm Kyowa Kirin Biologics Co. Ltd, licensed to Biocon Biologics Inc., a Biocon Biologics Company.
Copyright © 2023 Biocon Biologics Inc. All rights reserved.

PRINCIPAL DISPLAY PANEL – 40 mg/0.8 mL Syringe

NDC 83257-017-42

Hulio®

(adalimumab-fkjp) injection

40 mg/0.8 mL Syringe

FOR SUBCUTANEOUS USE ONLY

ATTENTION PHARMACIST: Each patient is required to receive the enclosed Medication Guide.

The entire carton is to be dispensed as a unit.
Return to pharmacy if dose tray seal is broken or missing.

2 Single-Dose
Preﬁlled Syringes

29 Gauge Needle

This carton contains:

- 2 dose trays (each containing
  1 single-dose preﬁlled syringe
  with 29 gauge 1/2 inch length
  ﬁxed needle)
- 2 alcohol preps
- 1 Quick Reference Guide
- 1 Instructions for Use
- 1 Medication Guide
- 1 Prescribing Information

Rx only

Each 0.8 mL single-dose prefilled syringe contains 40 mg of
adalimumab-fkjp, methionine (0.60 mg), monosodium glutamate
(1.50 mg), polysorbate 80 (0.80 mg), sorbitol (38.2 mg) and Water for
Injection, USP. Hydrochloric acid is added as necessary to adjust pH.

Contains no preservatives.

Prefilled syringe is for one time use only.
Dosage: See Prescribing Information.
Do not use beyond the expiration date.
Store in carton until time of administration with
protection from light.

Store in refrigerator at 36°F to 46°F (2°C to 8°C).

A HULIO prefilled syringe may be stored at room
temperature up to a maximum of 77°F (25°C) for up to
14 days with protection from light.

DO NOT FREEZE.

Manufactured by:
Biocon Biologics Inc.
245 Main St, 2nd Floor
Cambridge,MA 02142, U.S.A
U.S. License No. 2324
Product of Japan

HULIO® is a registered trademark of Fujifilm Kyowa Kirin Biologics Co. Ltd, licensed to Biocon Biologics Inc., a Biocon Biologics Company.
Copyright © 2023 Biocon Biologics Inc. All rights reserved.

PRINCIPAL DISPLAY PANEL – 40 mg/0.8 mL Pen

NDC 83257-019-32

Hulio® Pen

(adalimumab-fkjp) injection

40 mg/0.8 mL

FOR SUBCUTANEOUS USE ONLY

ATTENTION PHARMACIST: Each patient is required to receive the enclosed Medication Guide.

The entire carton is to be dispensed as a unit.
Return to pharmacy if dose tray seal is broken or missing.

29 Gauge Needle
2 Single-Dose Preﬁlled Pens

This carton contains:

- 2 dose trays (each containing
  1 single-dose preﬁlled syringe
  with 29 gauge 1/2 inch length
  ﬁxed needle)
- 2 alcohol preps
- 1 Quick Reference Guide
- 1 Instructions for Use
- 1 Medication Guide
- 1 Prescribing Information

Rx only

HULIO® is a registered trademark of Fujiﬁlm Kyowa Kirin Biologics Co. Ltd,
licensed to Biocon Biologics Inc., a Biocon Biologics Company.
Copyright © 2023 Biocon Biologics Inc. All rights reserved.

Each 0.8 mL single-dose preﬁlled pen contains 40 mg of adalimumab-fkjp,
methionine (0.60 mg), monosodium glutamate (1.50 mg), polysorbate 80
(0.80 mg), sorbitol (38.2 mg) and Water for Injection, USP. Hydrochloric acid
is added as necessary to adjust pH.

Contains no preservatives.

Preﬁlled pen is for one time use only.
Dosage: See Prescribing Information.
Do not use beyond the expiration date.
Store in carton until time of administration
with protection from light.
Store in refrigerator at 36°F to 46°F (2°C to 8°C).
A HULIO prefilled Pen may be stored at room
temperature up to a maximum of 77°F (25°C)
for up to 14 days with protection from light.

DO NOT FREEZE.

Manufactured by:
Biocon Biologics Inc.
245 Main St, 2nd Floor
Cambridge,MA 02142, U.S.A .
U.S. License No. 2324
Product of Japan